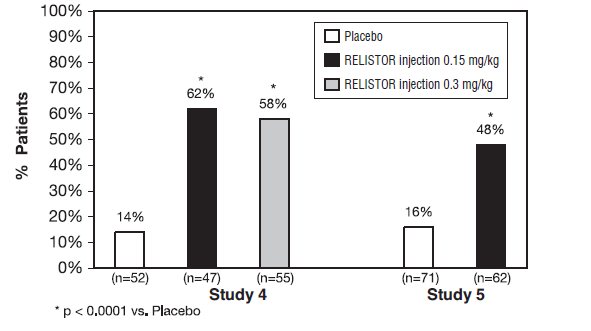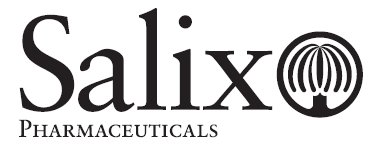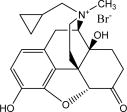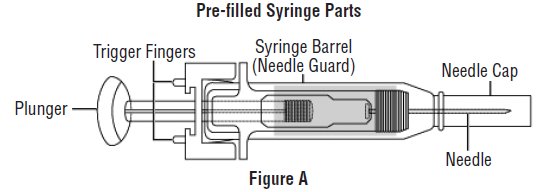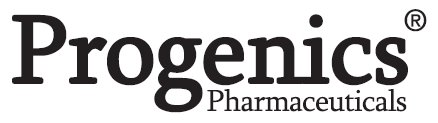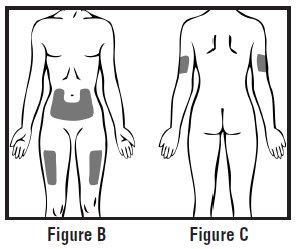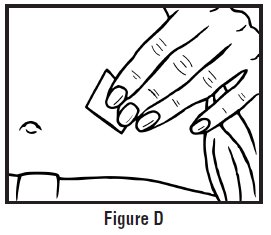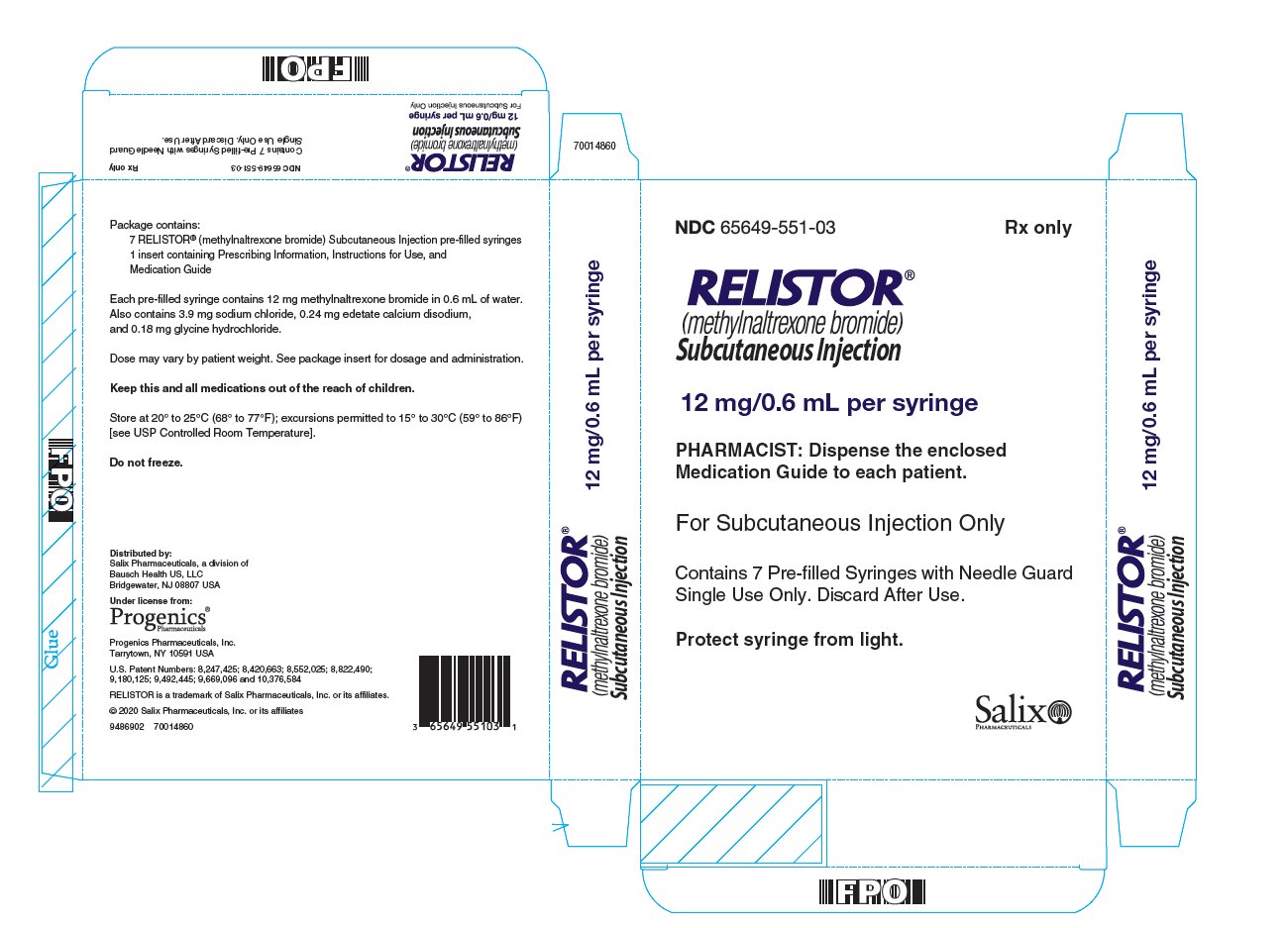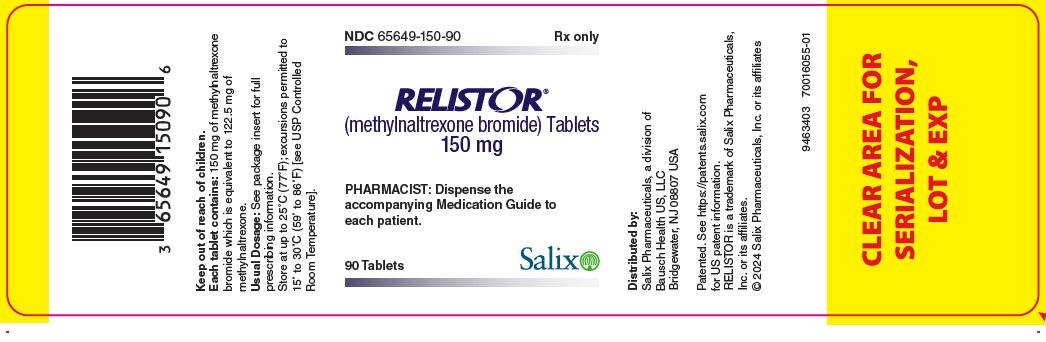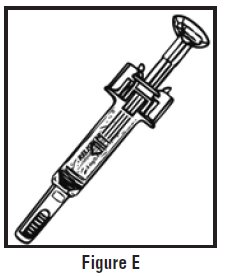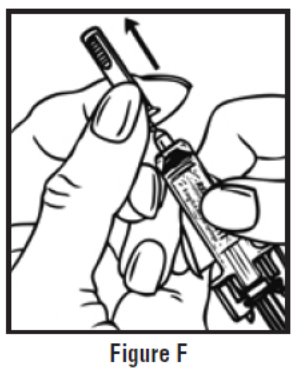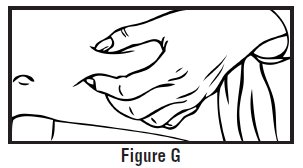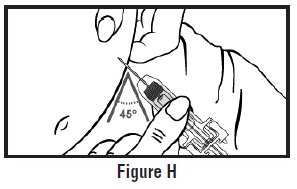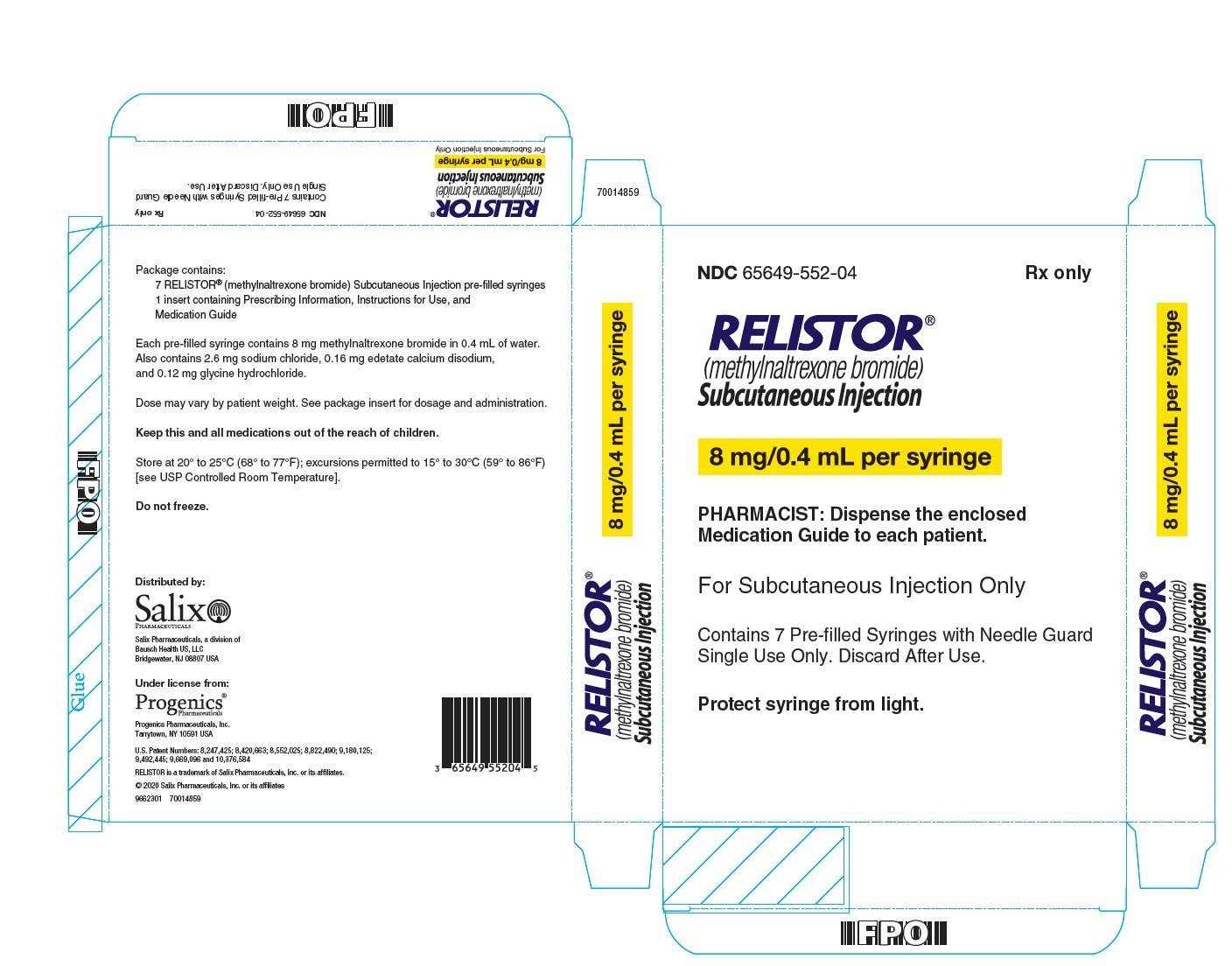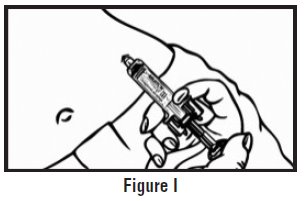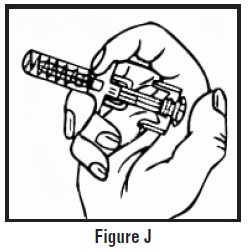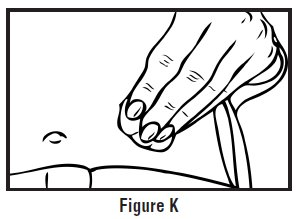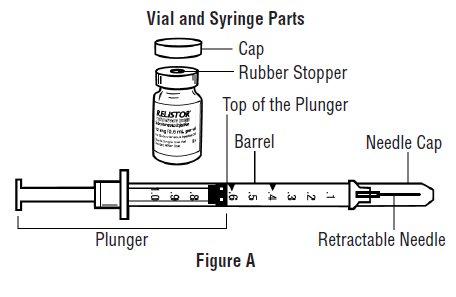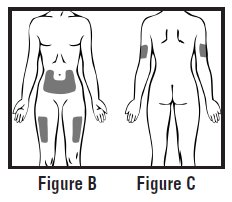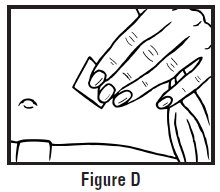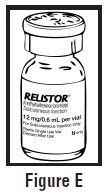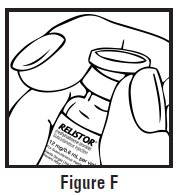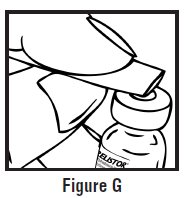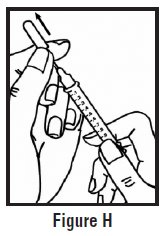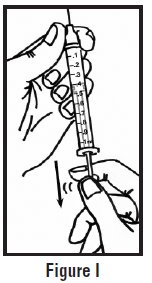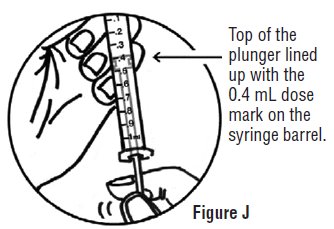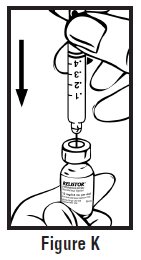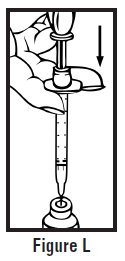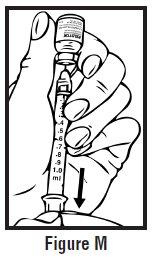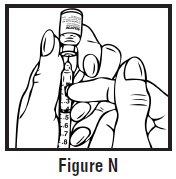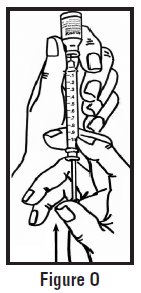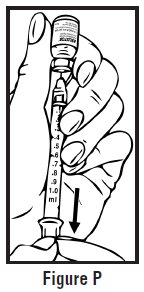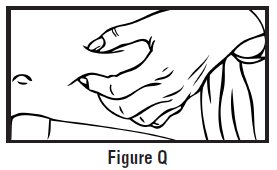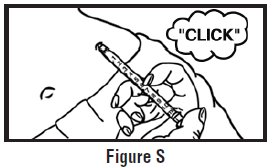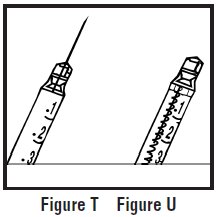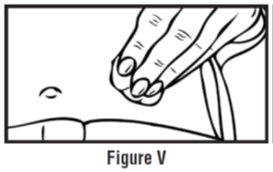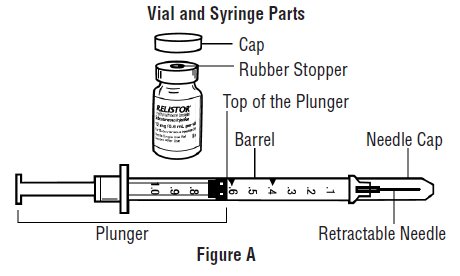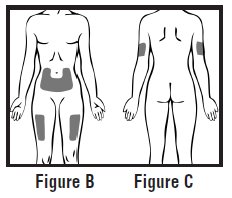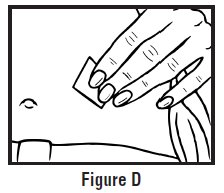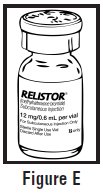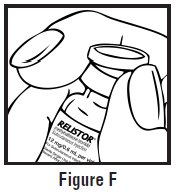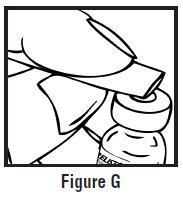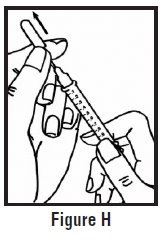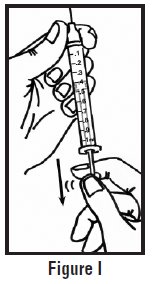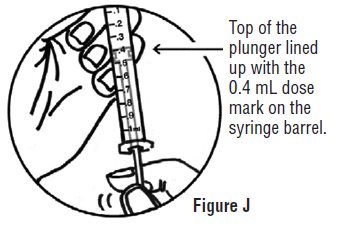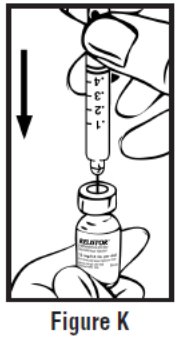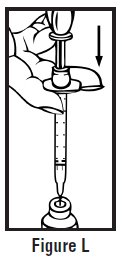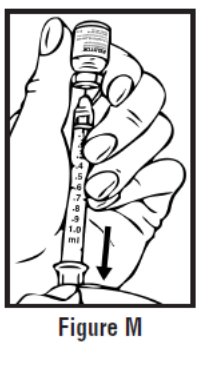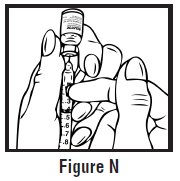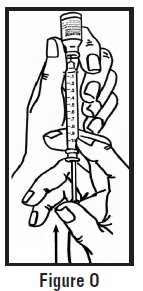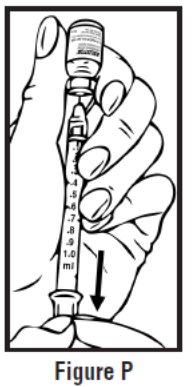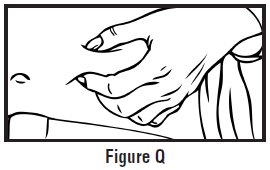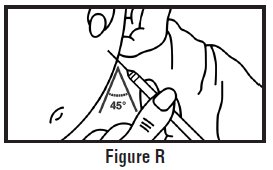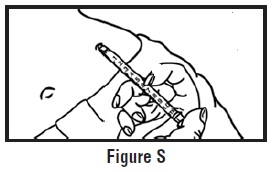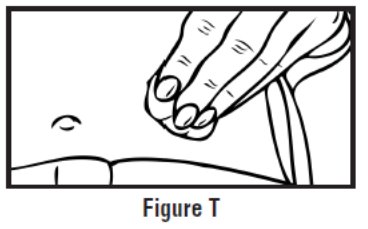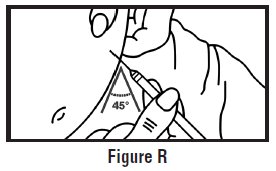 DRUG LABEL: Relistor
NDC: 65649-150 | Form: TABLET
Manufacturer: Salix Pharmaceuticals, Inc.
Category: prescription | Type: HUMAN PRESCRIPTION DRUG LABEL
Date: 20250611

ACTIVE INGREDIENTS: METHYLNALTREXONE BROMIDE 150 mg/1 1

HIGHLIGHTS OF PRESCRIBING INFORMATION

These highlights do not include all the information needed to use RELISTOR safely and effectively. See full prescribing information for RELISTOR.
RELISTOR®(methylnaltrexone bromide) tablets, for oral use
RELISTOR®(methylnaltrexone bromide) injection, for subcutaneous use
Initial U.S. Approval: 2008

1 INDICATIONS AND USAGE

- RELISTOR is an opioid antagonist. RELISTOR tablets and RELISTOR injection are indicated for the treatment of opioid-induced constipation (OIC) in adults with chronic non-cancer pain, including patients with chronic pain related to prior cancer or its treatment who do not require frequent (e.g., weekly) opioid dosage escalation. (1.1)
- RELISTOR injection is indicated for the treatment of OIC in adults with advanced illness or pain caused by active cancer who require opioid dosage escalation for palliative care. (1.2)

2 DOSAGE AND ADMINISTRATION

Administration Instructions (2.1)

- Be within close proximity to toilet facilities once administered.
- Discontinue if treatment with opioid pain medication is also discontinued.
- In adult patients with chronic non-cancer pain and OIC:
  - Patients receiving opioids for less than 4 weeks may be less responsive to RELISTOR.
  - Discontinue all maintenance laxative therapy before starting RELISTOR; may resume laxatives if there is a suboptimal response to RELISTOR after 3 days.
  - Re-evaluate the continued need for RELISTOR when opioid regimen is changed to avoid adverse reactions.
- In patients with chronic non-cancer pain and OIC, take RELISTOR tablets with water on an empty stomach at least 30 minutes before the first meal of the day.

Dosing

- For OIC in adult patients with chronic non-cancer pain (2.2):
  - RELISTOR tablets: The recommended dosage is 450 mg once daily in the morning.
  - RELISTOR injection: The recommended dosage is 12 mg subcutaneously once daily.
- For OIC in adult patients with advanced illness (2.3):
  - The pre-filled syringe is only for patients who require a RELISTOR injection dose of 8 mg or 12 mg. Use the vial for patients who require other doses of RELISTOR injection.
  - RELISTOR injection: See Table 1in the full prescribing information for the recommended dosage; administer one dose every other day, as needed, but no more frequently than one dose in a 24-hour period.

Dosage Adjustment

- See full prescribing information dosage adjustment in renal or hepatic impairment by indication. (2.4, 2.5)

Preparation and Administration of RELISTOR Injection(2.6)

- For subcutaneous use only.
- Inject in upper arm, abdomen or thigh. Rotate injection sites.

3 DOSAGE FORMS AND STRENGTHS

- Tablets: 150 mg methylnaltrexone bromide. (3)
- Injection:
  - 8 mg/0.4 mL methylnaltrexone bromide in single-dose pre-filled syringe. (3)
  - 12 mg/0.6 mL methylnaltrexone bromide in a single-dose pre-filled syringe, or single-dose vial. (3)

4 CONTRAINDICATIONS

Patients with known or suspected mechanical gastrointestinal obstruction and at increased risk of recurrent obstruction. (4, 5.1)

5 WARNINGS AND PRECAUTIONS

- Gastrointestinal Perforation: Consider the overall risk benefit in patients with known or suspected lesions of the GI tract. Monitor for severe, persistent or worsening abdominal pain; discontinue if development of symptoms. (5.1)
- Severe or Persistent Diarrhea: Discontinue if severe or persistent diarrhea occurs during treatment. (5.2)
- Opioid Withdrawal: Consider the overall risk benefit in patients with disruptions to the blood-brain barrier. Monitor closely for symptoms of opioid withdrawal. (5.3)

6 ADVERSE REACTIONS

The most common adverse reactions are:

OIC in adult patients with chronic non-cancer pain (6.1)

- RELISTOR tablets (≥ 2%): abdominal pain, diarrhea, headache, abdominal distention, vomiting, hyperhidrosis, anxiety, muscle spasms, rhinorrhea, and chills.
- RELISTOR injection (≥ 1%): abdominal pain, nausea, diarrhea, hyperhidrosis, hot flush, tremor, and chills.

OIC in adult patients with advanced illness(6.1)

- RELISTOR injection (≥ 5%): abdominal pain, flatulence, nausea, dizziness, and diarrhea.

To report SUSPECTED ADVERSE REACTIONS, contact Salix Pharmaceuticals at 1-800-321-4576 or FDA at 1-800-FDA-1088 or www.fda.gov/medwatch.

7 DRUG INTERACTIONS

- Other Opioid Antagonists: Potential for additive effect and increased risk of opioid withdrawal; avoid concomitant use. (7.1)

8 USE IN SPECIFIC POPULATIONS

- Pregnancy: May precipitate opioid withdrawal in a fetus (8.1)
- Lactation: Breastfeeding not recommended. (8.2)

FULL PRESCRIBING INFORMATION

1 INDICATIONS AND USAGE

1.1 Opioid-Induced Constipation in Adult Patients with Chronic Non-Cancer Pain

RELISTOR tablets and RELISTOR injection are indicated for the treatment of opioid-induced constipation (OIC) in adult patients with chronic non-cancer pain, including patients with chronic pain related to prior cancer or its treatment who do not require frequent (e.g., weekly) opioid dosage escalation.

1.2 Opioid-Induced Constipation in Adult Patients with Advanced Illness

RELISTOR injection is indicated for the treatment of OIC in adult patients with advanced illness or pain caused by active cancer who require opioid dosage escalation for palliative care.

2 DOSAGE AND ADMINISTRATION

2.1 Important Administration Information

- Be within close proximity to toilet facilities once RELISTOR is administered.
- Discontinue RELISTOR if treatment with the opioid pain medication is also discontinued.
- In adult patients with chronic non-cancer pain and OIC:
  - Patients receiving opioids for less than 4 weeks may be less responsive to RELISTOR [see Clinical Studies (14.1)].
  - Discontinue all maintenance laxative therapy prior to initiation of RELISTOR. Laxative(s) can be used as needed if there is a suboptimal response to RELISTOR after three days.
  - Re-evaluate the continued need for RELISTOR when the opioid regimen is changed to avoid adverse reactions.
  - In patients with chronic non-cancer pain and OIC, take RELISTOR tablets with water on an empty stomach at least 30 minutes before the first meal of the day.

2.2 Opioid-Induced Constipation in Adult Patients with Chronic Non-Cancer Pain

- The recommended dosage of RELISTOR tablets is 450 mg taken orally once daily in the morning.
- The recommended dosage of RELISTOR injection is 12 mg administered subcutaneously once daily.

2.3 Opioid-Induced Constipation in Adult Patients with Advanced Illness

The pre-filled syringe is only for patients who require a RELISTOR injection dose of 8 mg or 12 mg. Use the vial for patients who require other doses of RELISTOR injection.

Table 1below shows the recommended weight-based dose of RELISTOR injection and the corresponding injection volume. The recommended dosage regimen is one dose administered subcutaneously every other day, as needed. Do not administer more frequently than one dose per 24-hour period.

Table 1: Weight-Based Dosing of RELISTOR Injection and Corresponding Injection Volume for Adult Patients with OIC and Advanced Illness
Weight of Adult Patient | Subcutaneous; Dose | Injection Volume
Less than 38 kg | 0.15 mg/kg | See below*
38 kg to less than 62 kg | 8 mg | 0.4 mL
62 kg to 114 kg | 12 mg | 0.6 mL
More than 114 kg | 0.15 mg/kg | See below*
*Calculate the injection volume for these patients by multiplying the patient weight in kilograms by 0.0075 and then rounding up the volume to the nearest 0.1 mL.

2.4 Dosage in Patients with Renal Impairment

The recommended dosage of RELISTOR in patients with moderate and severe renal impairment (i.e., creatinine clearance less than 60 mL/minute as estimated by Cockcroft-Gault) [see Use in Specific Populations (8.6)] , is shown below by indication:

OIC in Adult Patients with Chronic Non- Cancer Pain

- RELISTOR tablets: 150 mg once daily in the morning.
- RELISTOR injection: 6 mg administered subcutaneously once daily

OIC in Adult Patients with Advanced Illness

RELISTOR injection: The recommended dosage regimen is one dose every other day, as needed is shown in Table 2.

Table 2: Weight-Based Dosing in Moderate and Severe Renal Impairment of RELISTOR Injection and Corresponding Injection Volume for Adult Patients with OIC and Advanced Illness
Weight of Adult Patient | Subcutaneous Dose | Injection Volume
Less than 38 kg | 0.075 mg/kg | See below*
38 kg to less than 62 kg | 4 mg | 0.2 mL
62 kg to 114 kg | 6 mg | 0.3 mL
More than 114 kg | 0.075 mg/kg | See below*

*Calculate the injection volume for these patients by multiplying the patient weight in kilograms by 0.00375 and then rounding up the volume to the nearest 0.1 mL.

2.5 Dosage in Patients with Hepatic Impairment

OIC in Adult Patients with Chronic Non-Cancer Pain

- RELISTOR tablets: The recommended dosage in adult patients with moderate or severe hepatic impairment (Child-Pugh Class B or C) is 150 mg, once daily in the morning [ see Use in Specific Populations (8.7)].
- RELISTOR injection: If considering dose adjustment for patients with severe hepatic impairment, follow the recommendations in Table 3 [see Use in Specific Populations (8.7)].

Table 3: Weight-Based Dosing in Severe Hepatic Impairment of RELISTOR Injection and
Corresponding Injection Volume for Adult Patients with OIC and Chronic Non-Cancer Pain
Weight of Adult Patient | Subcutaneous Dose | Injection Volume
Less than 38 kg | 0.075 mg/kg | See below*
38 kg to less than 62 kg | 4 mg | 0.2 mL
62 kg to 114 kg | 6 mg | 0.3 mL
More than 114 kg | 0.075 mg/kg | See below*

* Calculate the injection volume for these patients by multiplying the patient weight in kilograms by 0.00375 and then rounding up the volume to the nearest 0.1 mL.

2.6 Preparation and Administration of RELISTOR Injection

- RELISTOR injection is for subcutaneous use only.
- Single-dose pre-filled syringes: Do not remove the pre-filled syringe from the tray until ready to administer.
- Inspect RELISTOR injection visually for particulate matter and discoloration prior to administration. RELISTOR injection is colorless to pale yellow. Discard the pre-filled syringe or vial if particulate matter or discoloration is present.
- Administer RELISTOR injection subcutaneously in the upper arm, abdomen or thigh. Do not inject at the same spot each time (rotate injection sites).
- RELISTOR single-dose vials: Once drawn into the syringe, if immediate administration is not possible, store at ambient room temperature and administer within 24 hours. Discard any unused portion that remains in the vial.
- For patient or caregiver instructions for preparation and administration of RELISTOR injection (including recommended specifications for the syringe and needle to be used with the single-dose vial), see Instructions for Use.

3 DOSAGE FORMS AND STRENGTHS

- Tablets:
- 150 mg methylnaltrexone bromide supplied as film-coated, white, round, biconvex, debossed with “REL” on one side and plain on the other side.

Injection:

Single-dose Vial:

- 12 mg/0.6 mL methylnaltrexone bromide supplied as colorless to pale yellow solution.

Single-dose Pre-filled Syringe:

- 8 mg/0.4 mL methylnaltrexone bromide supplied as colorless to pale yellow solution.
- 12 mg/0.6 mL methylnaltrexone bromide supplied as colorless to pale yellow solution.

4 CONTRAINDICATIONS

RELISTOR is contraindicated in patients with known or suspected gastrointestinal obstruction and patients at increased risk of recurrent obstruction, due to the potential for gastrointestinal perforation [see Warnings and Precautions (5.1)] .

5 WARNINGS AND PRECAUTIONS

5.1 Gastrointestinal Perforation

Cases of gastrointestinal perforation have been reported in adult patients with OIC and advanced illness with conditions that may be associated with localized or diffuse reduction of structural integrity in the wall of the gastrointestinal tract (e.g., peptic ulcer disease, Ogilvie’s syndrome, diverticular disease, infiltrative gastrointestinal tract malignancies or peritoneal metastases). Take into account the overall risk-benefit profile when using RELISTOR in patients with these conditions or other conditions which might result in impaired integrity of the gastrointestinal tract wall (e.g., Crohn’s disease). Monitor for the development of severe, persistent, or worsening abdominal pain; discontinue RELISTOR in patients who develop this symptom [see Contraindications (4)].

5.2 Severe or Persistent Diarrhea

If severe or persistent diarrhea occurs during treatment, advise patients to discontinue therapy with RELISTOR and consult their healthcare provider.

5.3 Opioid Withdrawal

Symptoms consistent with opioid withdrawal, including hyperhidrosis, chills, diarrhea, abdominal pain, anxiety, and yawning have occurred in patients treated with RELISTOR [see Adverse Reactions (6.1)] . Patients having disruptions to the blood-brain barrier may be at increased risk for opioid withdrawal and/or reduced analgesia. Take into account the overall risk-benefit profile when using RELISTOR in such patients. Monitor for adequacy of analgesia and symptoms of opioid withdrawal in such patients.

6 ADVERSE REACTIONS

Serious and important adverse reactions described elsewhere in the labeling include:

- Gastrointestinal perforation [see Warnings and Precautions (5.1)]
- Severe or persistent diarrhea [see Warnings and Precautions (5.2)]
- Opioid withdrawal [see Warnings and Precautions (5.3)]

6.1 Clinical Trials Experience

Because clinical trials are conducted under widely varying conditions, adverse reaction rates observed in the clinical trials of a drug cannot be directly compared to rates in the clinical trials of another drug and may not reflect the rates observed in clinical practice.

Opioid-Induced Constipation in Adult Patients with Chronic Non-Cancer Pain

The safety of RELISTOR tablets was evaluated in a double-blind, placebo-controlled trial in adult patients with OIC and chronic non-cancer pain receiving opioid analgesia. This study (Study 1) included a 12-week, double-blind, placebo-controlled period in which adult patients were randomized to receive RELISTOR tablets 450 mg orally (200 patients) or placebo (201 patients) [see Clinical Studies(14.1) ]. After 4 weeks of double-blind treatment administered once daily, patients continued 8 weeks of double-blind treatment on an as needed basis (but not more than once daily).

The most common adverse reactions in adult patients with OIC and chronic non-cancer pain receiving RELISTOR tablets are shown in Table 4. Adverse reactions of abdominal pain, diarrhea, hyperhidrosis, anxiety, rhinorrhea, and chills may reflect symptoms of opioid withdrawal.

Table 4: Adverse Reactions* in 4-Week Double-Blind, Placebo-Controlled Period of Clinical Study of RELISTOR Tablets in Adult Patients with OIC and Chronic Non-Cancer Pain (Study 1)
Adverse Reaction | RELISTOR Tablets n = 200 | Placebo n = 201
Abdominal Pain** | 14% | 10%
Diarrhea | 5% | 2%
Headache | 4% | 3%
Abdominal Distention | 4% | 2%
Vomiting | 3% | 2%
Hyperhidrosis | 3% | 1%
Anxiety | 2% | 1%
Muscle Spasms | 2% | 1%
Rhinorrhea | 2% | 1%
Chills | 2% | 0%

The safety of RELISTOR injection was evaluated in a double-blind, placebo-controlled trial in adult patients with OIC and chronic non-cancer pain receiving opioid analgesia. This study (Study 2) included a 4-week, double-blind, placebo-controlled period in which adult patients were randomized to receive RELISTOR injection 12 mg subcutaneously once daily (150 patients) or placebo (162 patients) [see Clinical Studies (14.1)] . After 4 weeks of double-blind treatment, patients began an 8‑week open-label treatment period during which RELISTOR injection 12 mg subcutaneously was administered less frequently than the recommended dosage regimen of 12 mg once daily.

The most common adverse reactions in adult patients with OIC and chronic non-cancer pain receiving RELISTOR injection are shown in Table 5. The adverse reactions in the table below may reflect symptoms of opioid withdrawal.

Table 5: Adverse Reactions* in 4-Week Double-Blind, Placebo-Controlled Period of Clinical Study of RELISTOR Injection in Adult Patients with OIC and Chronic Non-Cancer Pain (Study 2)
Adverse Reaction | RELISTOR Injection n = 150 | Placebo n = 162
Abdominal Pain** | 21% | 7%
Nausea | 9% | 6%
Diarrhea | 6% | 4%
Hyperhidrosis | 6% | 1%
Hot Flush | 3% | 2%
Tremor | 1% | <1%
Chills | 1% | 0%

* Adverse reactions occurring in at least 1% of patients receiving RELISTOR injection 12 mg subcutaneously once daily and at an incidence greater than placebo.

** Includes: abdominal pain, upper abdominal pain, lower abdominal pain, abdominal discomfort and abdominal tenderness

During the 4-week double-blind period, in patients with OIC and chronic non-cancer pain that received RELISTOR every other day, there was a higher incidence of adverse reactions, including nausea (12%), diarrhea (12%), vomiting (7%), tremor (3%), feeling of body temperature change (3%), piloerection (3%), and chills (2%) as compared to daily RELISTOR dosing. Use of RELISTOR injection 12 mg subcutaneously every other day is not recommended in patients with OIC and chronic non-cancer pain [see Dosage and Administration (2.2)]. The rates of discontinuation due to adverse reactions during the double-blind period (Study 2) were higher in the RELISTOR once daily (7%) than the placebo group (3%). Abdominal pain was the most common adverse reaction resulting in discontinuation from the double-blind period in the RELISTOR once daily group (2%).

The safety of RELISTOR injection was also evaluated in a 48-week, open-label, uncontrolled trial in 1034 adult patients with OIC and chronic non-cancer pain (Study 3). Patients were allowed to administer RELISTOR injection 12 mg subcutaneously less frequently than the recommended dosage regimen of 12 mg once daily, and took a median of 6 doses per week. A total of 624 patients (60%) completed at least 24 weeks of treatment and 477 (46%) completed the 48‑week study. The adverse reactions seen in this study were similar to those observed during the 4-week double-blind period of Study 2. Additionally, in Study 3, investigators reported 4 myocardial infarctions (1 fatal), 1 stroke (fatal), 1 fatal cardiac arrest and 1 sudden death. It is not possible to establish a relationship between these events and RELISTOR.

Opioid-Induced Constipation in Adult Patients with Advanced Illness

The safety of RELISTOR injection was evaluated in two, double-blind, placebo-controlled trials in adult patients with OIC and advanced illness receiving palliative care: Study 4 included a single-dose, double-blind, placebo-controlled period, whereas Study 5 included a 14-day multiple dose, double-blind, placebo-controlled period [see Clinical Studies (14.2) ].

The most common adverse reactions in adult patients with OIC and advanced illness receiving RELISTOR injection are shown in Table 6below.

Table 6: Adverse Reactions from All Doses in Double-Blind, Placebo-Controlled Clinical Studies of RELISTOR Injection in Adult Patients with OIC and Advanced Illness* (Studies 4 and 5)
Adverse Reaction | RELISTOR Injection n = 165 | Placebo n = 123
Abdominal Pain ** | 29% | 10%
Flatulence | 13% | 6%
Nausea | 12% | 5%
Dizziness | 7% | 2%
Diarrhea | 6% | 2%

* Adverse reactions occurring in at least 5% of patients receiving all doses of RELISTOR injection (0.075, 0.15, and 0.3 mg/kg) and at an incidence greater than placebo

** Includes: abdominal pain, upper abdominal pain, lower abdominal pain, abdominal discomfort and abdominal tenderness

The rates of discontinuation due to adverse reactions during the double-blind, placebo-controlled clinical trials (Study 4 and Study 5) were comparable between RELISTOR (1%) and placebo (2%).

6.2 Postmarketing Experience

The following adverse reactions have been identified during post-approval use of RELISTOR injection. Because reactions are reported voluntarily from a population of uncertain size, it is not always possible to reliably estimate the frequency or establish a causal relationship to drug exposure.

Gastrointestinal

Perforation, cramping, vomiting

General Disorders and Administration Site Disorders

Diaphoresis, flushing, malaise, pain. Cases of opioid withdrawal have been reported [see Warnings and Precautions (5.3)].

7 DRUG INTERACTIONS

7.1 Other Opioid Antagonists

Avoid concomitant use of RELISTOR with other opioid antagonists because of the potential for additive effects of opioid receptor antagonism and increased risk of opioid withdrawal.

7.2 Drugs Metabolized by Cytochrome P450 Isozymes

In healthy subjects, a subcutaneous dose of 0.3 mg/kg of RELISTOR did not significantly affect the metabolism of dextromethorphan, a CYP2D6 substrate.

8 USE IN SPECIFIC POPULATIONS

8.1 Pregnancy

Risk Summary

The limited available data with RELISTOR in pregnant women are not sufficient to inform a drug-associated risk for major birth defects and miscarriages. There are clinical considerations when RELISTOR is used by pregnant women [see Clinical Considerations].In animal reproduction studies, no effects on embryofetal development were observed with the administration of intravenous methylnaltrexone bromide during organogenesis in rats and rabbits at doses up to 20 times and 26 times, respectively, the subcutaneous maximum recommended human dose (MRHD) of 12 mg RELISTOR injection per day. The intravenous doses in rats and rabbits are about 0.5 times and 0.7 times, respectively, the oral MRHD of 450 mg/day [see Data].Advise pregnant women of the potential risk to a fetus.

The estimated background risk of major birth defects and miscarriage for the indicated population is unknown. In the U.S. general population, the estimated background risk of major birth defects and miscarriage in clinically recognized pregnancies is 2 to 4% and 15 to 20%, respectively.

Clinical Considerations

Fetal/Neonatal Adverse Reactions

The use of RELISTOR during pregnancy may precipitate opioid withdrawal in a fetus due to the immature fetal blood-brain barrier.

Data

Animal Data

Reproduction studies have been performed with methylnaltrexone bromide administered during the period of organogenesis to rats at intravenous doses up to 25 mg/kg/day (about 20 times the subcutaneous MRHD of 12 mg/day based on body surface area), and did not cause any adverse effects on embryofetal development. In rabbits, intravenous doses of methylnaltrexone bromide up to 16 mg/kg/day (about 26 times the subcutaneous MRHD of 12 mg/day) did not show any embryofetal toxicity. The intravenous doses in rats (25 mg/kg/day) and rabbits (16 mg/kg/day) are about 0.5 and 0.7 times, respectively, the oral MRHD of 450 mg/day based on body surface area. A pre- and postnatal development study in rats showed no evidence of any adverse effect on pre- and postnatal development at subcutaneous doses of methylnaltrexone bromide up to 100 mg/kg/day (about 81 times the subcutaneous MRHD of 12 mg/day; about 2.2 times the oral MRHD of 450 mg/day).

8.2 Lactation

Risk Summary

There is no information regarding the presence of methylnaltrexone in human milk, the effects on the breastfed infant, or the effects on milk production. Methylnaltrexone is present in rat milk [see Data].Because of the potential for serious adverse reactions, including opioid withdrawal, in breastfed infants, advise women that breastfeeding is not recommended during treatment with RELISTOR.

Data

Radioactivity appeared in rat milk within 30 minutes of a single subcutaneous administration of radiolabeled methylnaltrexone bromide and was concentrated up to 24-fold at 8 hours after administration relative to plasma concentrations.

8.4 Pediatric Use

Safety and effectiveness of RELISTOR tablets and injection have not been established in pediatric patients.

Juvenile Animal Studies

In juvenile rats administered intravenous methylnaltrexone bromide for 13 weeks, adverse clinical signs such as convulsions, tremors and labored breathing were observed, and the juvenile rats were found to be more sensitive to the adverse effects of methylnaltrexone when compared to adult animals. Juvenile dogs administered intravenous methylnaltrexone bromide for 13 weeks had a toxicity profile similar to adult dogs [see Nonclinical Toxicology (13.2)].

8.5 Geriatric Use

Of the total number of patients in clinical studies of RELISTOR tablets, a total of 136 patients (10%) were aged 65 years and older, while 23 (2%) were aged 75 and older. In clinical studies of RELISTOR tablets, no overall differences in effectiveness were observed. Adverse reactions were similar; however, there was a higher incidence of diarrhea in elderly patients.

Of the total number of patients in clinical studies of RELISTOR injection, a total of 226 (28%) were aged 65 years and older, while 108 (13%) were aged 75 years and older. In clinical studies of RELISTOR injection, no overall differences in safety or effectiveness were observed between elderly patients and younger patients.

Based on pharmacokinetic data, and safety and efficacy data from controlled clinical trials, no dosage adjustment based on age is recommended. Monitor elderly patients for adverse reactions.

8.6 Renal Impairment

In a study of subjects with varying degrees of renal impairment receiving RELISTOR injection subcutaneously, there was a significant increase in the exposure to methylnaltrexone in subjects with moderate and severe renal impairment (creatinine clearance less than 60 mL/minute as estimated by Cockcroft-Gault) compared to healthy subjects [see Clinical Pharmacology (12.3)] .

Therefore, a dosage reduction of RELISTOR tablets and RELISTOR injection is recommended in patients with moderate and severe renal impairment [see Dosage and Administration (2.4)] . No dosage adjustment of RELISTOR tablets or RELISTOR injection is needed in patients with mild renal impairment (creatinine clearance greater than 60 mL/minute as estimated by Cockcroft-Gault).

8.7 Hepatic Impairment

Tablets

In a study of subjects with varying degrees of hepatic impairment receiving a 450 mg dose of RELISTOR tablets, there was a significant increase in systemic exposure of methylnaltrexone for subjects with moderate (Child-Pugh Class B) and severe (Child-Pugh Class C) hepatic impairment compared to healthy subjects with normal hepatic function [see Clinical Pharmacology (12.3)] . Therefore, a dosage reduction of RELISTOR tablets is recommended in patients with moderate or severe hepatic impairment [see Dosage and Administration (2.4)]. No dosage adjustment of RELISTOR tablets is needed in patients with mild hepatic impairment (Child-Pugh Class A).

Injection

In a study of subjects with mild or moderate hepatic impairment, there was no clinically meaningful change in systemic exposure of methylnaltrexone compared to healthy subjects with normal hepatic function [see Clinical Pharmacology (12.3)] . Therefore, no dosage adjustment of RELISTOR injection is needed for patients with mild or moderate hepatic impairment [see Clinical Pharmacology (12.3)].

Patients with severe hepatic impairment were not studied. In patients with severe hepatic impairment, monitor for methylnaltrexone-related adverse reactions. If considering dosage adjustment, follow the recommendations in Table 3 [see Dosage and Administration (2.5)].

10 OVERDOSAGE

During clinical trials of RELISTOR administered orally and subcutaneously, one accidental case of methylnaltrexone bromide overdose was reported and no adverse events were reported as a result of the overdosage.

A study of healthy subjects noted orthostatic hypotension associated with a dose of 0.64 mg/kg administered as an intravenous bolus. Monitor for signs or symptoms of orthostatic hypotension and initiate treatment as appropriate.

If a patient on opioid therapy receives an overdose of RELISTOR, the patient should be monitored closely for potential evidence of opioid withdrawal symptoms such as chills, rhinorrhea, diaphoresis or reversal of central analgesic effect. Base treatment on the degree of opioid withdrawal symptoms, including changes in blood pressure and heart rate, and on the need for analgesia.

11 DESCRIPTION

RELISTOR®(methylnaltrexone bromide) is a mu-opioid receptor antagonist. The chemical name for methylnaltrexone bromide is (R)- N-(cyclopropylmethyl) noroxymorphone methobromide. The molecular formula is C21H26NO4Br, and the molecular weight is 436.36.

The structural formula is:

RELISTOR tablets for oral administration are film-coated and contain 150 mg of methylnaltrexone bromide (equivalent to 122.5 mg methylnaltrexone). Inactive ingredients are silicified microcrystalline cellulose, microcrystalline cellulose, sodium lauryl sulfate, croscarmellose sodium, crospovidone, poloxamer 407, stearic acid (vegetable source), colloidal silicon dioxide, edetate calcium disodium, polyvinyl alcohol, titanium dioxide, polyethylene glycol and talc.

RELISTOR for subcutaneous administration is a sterile, clear and colorless to pale yellow aqueous solution. Each 3 mL vial contains 12 mg of methylnaltrexone bromide (equivalent to 9.8 mg of methylnaltrexone) in 0.6 mL of water. The excipients are 3.9 mg sodium chloride USP, 0.24 mg edetate calcium disodium USP, and 0.18 mg glycine hydrochloride. During manufacture, the pH may have been adjusted with hydrochloric acid and/or sodium hydroxide.

Each 8 mg/0.4 mL pre-filled syringe (1 mL syringe) contains 8 mg of methylnaltrexone bromide (equivalent to 6.5 mg of methylnaltrexone) in 0.4 mL of water. The excipients are 2.6 mg sodium chloride USP, 0.16 mg edetate calcium disodium USP, and 0.12 mg glycine hydrochloride.

Each 12 mg/0.6 mL pre-filled syringe (1 mL syringe) contains 12 mg of methylnaltrexone bromide (equivalent to 9.8 mg of methylnaltrexone) in 0.6 mL of water. The excipients are 3.9 mg sodium chloride USP, 0.24 mg edetate calcium disodium USP, and 0.18 mg glycine hydrochloride.

12 CLINICAL PHARMACOLOGY

12.1 Mechanism of Action

Methylnaltrexone is a selective antagonist of opioid binding at the mu-opioid receptor. As a quaternary amine, the ability of methylnaltrexone to cross the blood-brain barrier is restricted. This allows methylnaltrexone to function as a peripherally-acting mu-opioid receptor antagonist in tissues such as the gastrointestinal tract, thereby decreasing the constipating effects of opioids without impacting opioid-mediated analgesic effects on the central nervous system (CNS).

12.2 Pharmacodynamics

Cardiac Electrophysiology

In a randomized, double-blind placebo- and (open-label) moxifloxacin-controlled 4-period crossover study, 56 healthy subjects were administered methylnaltrexone bromide 0.3 mg/kg and methylnaltrexone bromide 0.64 mg/kg by intravenous infusion over 20 minutes (RELISTOR is not approved for intravenous use), placebo, and a single oral dose of moxifloxacin. At a dose approximately 4.3 times the maximum recommended dose (7.5 times the mean peak plasma concentration for RELISTOR injection and 22 times the peak plasma concentration for RELISTOR tablets), methylnaltrexone does not prolong the QTc interval to any clinically relevant extent.

12.3 Pharmacokinetics

Between the oral dosage range of 150 mg to 450 mg for RELISTOR tablets and the subcutaneous dosage range of 0.15 mg/kg to 0.50 mg/kg for RELISTOR injection, the mean Cmaxand area under the plasma concentration-time curve (AUC) of methylnaltrexone increased in a dose-proportional manner. There was no significant accumulation of methylnaltrexone following once-daily oral dosing of 450 mg RELISTOR tablets or subcutaneous dosing of 12 mg RELISTOR injection for seven consecutive days in healthy subjects.

Absorption

Tablets

Following administration of a single 450 mg dose of RELISTOR tablets in OIC patients or healthy subjects, peak concentrations (Cmax) of methylnaltrexone were observed at approximately 1.5 hours. The absolute bioavailability of oral methylnaltrexone bromide has not been determined. The Cmaxand AUC in healthy subjects were 48.1 ng/mL and 382 ng·hr/mL, respectively, following a single 450 mg dose of RELISTOR tablets. Exposure in the OIC patient population was approximately 27% lower than in healthy subjects.

Food Effect

Administration of a single 450 mg dose of RELISTOR tablets to healthy subjects with a high-fat breakfast (containing approximately 800 to 1000 total calories, with 60%, 25% and 15% of calories derived from fat, carbohydrate and protein, respectively) resulted in a decrease in the Cmaxof methylnaltrexone by 60%, the AUC by 43% and delayed the Tmaxby 2 hours [see Dosage and Administration (2.1)] .

Injection

Following administration of RELISTOR injection subcutaneously, methylnaltrexone achieved peak concentrations (Cmax) at approximately 0.5 hours (see Table 7).

Table 7: Pharmacokinetic Parameters of Methylnaltrexone Following Subcutaneous Doses
Parameter | 0.15 mg/kg; Single Dose | 12 mg; Single Dose | 12 mg; at Steady-State
Cmax(ng/mL)i | 117 (32.7) | 140 (35.6) | 119 (27.2)
Tmax(hr)ii | 0.5 (0.25 to 0.75) | 0.25 (0.25 to 0.5) | 0.25 (0.25 to 0.5)
AUC24(ng·hr/mL)i | 175 (36.6) | - (28.3) | - 223 (28.2)

Distribution

The steady-state volume of distribution (Vss) of methylnaltrexone is approximately 1.1 L/kg. The fraction of methylnaltrexone bound to human plasma proteins is 11% to 15%, as determined by equilibrium dialysis.

Elimination

Following oral administration of a single 450 mg dose of RELISTOR tablets, concentrations of methylnaltrexone declined in multiphasic manner with a terminal half-life (t1/2) of approximately 15 hours.

Metabolism

In an intravenous mass balance study, approximately 44% of the administered radioactivity was recovered in the urine over 24 hours with 5 distinct metabolites. None of the detected metabolites was in amounts over 6% of administered radioactivity. Conversion to methyl-6-naltrexol isomers (5% of total) and methylnaltrexone sulfate (1% of total) appear to be the primary pathways of metabolism. N-demethylation of methylnaltrexone to produce naltrexone is not significant.

Systemic exposure of methylnaltrexone metabolites after oral administration of a single 450 mg dose of RELISTOR tablets are greater than the systemic exposure of methylnaltrexone metabolites after subcutaneous administration of a single 12 mg dose of RELISTOR injection. Subcutaneous administration is not subject to first-pass hepatic metabolism prior to appearance in the systemic circulation. After 12 mg subcutaneous once daily dosing the mean AUC0-24ratio of metabolites to methylnaltrexone at steady-state was 30%, 19%, and 9% for methylnaltrexone sulfate, methyl-6α-naltrexol, and methyl-6β-naltrexol, respectively. After 450 mg oral once daily dosing, the ratio of the mean AUC0-24of metabolites to methylnaltrexone at steady-state was 79%, 38%, and 21% for methylnaltrexone sulfate, methyl-6α-naltrexol, and methyl-6β-naltrexol, respectively. Methylnaltrexone sulfate is a weak mu-opioid receptor antagonist; methyl-6α-naltrexol, and methyl-6β-naltrexol are active mu-opioid receptor antagonists.

Methylnaltrexone is conjugated by sulfotransferase SULT1E1 and SULT2A1 isoforms to methylnaltrexone sulfate. Conversion to methyl-6-naltrexol isomers is mediated by aldo-keto reductase 1C enzymes.

Excretion

In an intravenous mass balance study, approximately half of the dose was excreted in the urine (54%), and 17% of administered dose was excreted in the feces up to 168 hours postdose; however, radiolabeled recovery in this study was only 71% after 7 days. Methylnaltrexone is excreted primarily as the unchanged drug in the urine and feces. Active renal secretion of methylnaltrexone is suggested by renal clearance of methylnaltrexone that is approximately 4- to 5-fold higher than creatinine clearance.

No mass balance clinical studies were conducted with oral administration of methylnaltrexone bromide. However, following once daily dosing of 450 mg RELISTOR tablets for 1 week, the percentage of dose recovered in the urine as the parent methylnaltrexone was low (approximately 1% on both Day 1 and Day 7).

Specific Populations

Age: Geriatric Population

A study was conducted to characterize the pharmacokinetics of methylnaltrexone after a single dose of 24 mg methylnaltrexone bromide via intravenous infusion over 20 min in healthy adults between 18 and 45 years of age and in healthy adults aged 65 years and older. In elderly subjects (mean age 72 years old), mean clearance was about 20% lower (56 L/h versus 70 L/h) and AUC∞was 26% higher than in subjects between 18 and 45 years of age (mean age 30 years old) [s ee Use in Specific Populations (8.5)].

Renal Impairment

Administration of a single subcutaneous dose of 0.3 mg/kg of RELISTOR injection in subjects with varying degrees of renal impairment (8 subjects each cohort) resulted in a 1.3-, 1.7- and 1.9-fold higher AUC0-∞of methylnaltrexone, respectively, compared to 8 subjects with normal renal function [ see Dosage and Administration (2.4)].The mean Cmaxdid not change significantly with renal impairment. No studies were performed in patients with end-stage renal impairment requiring dialysis.

Hepatic Impairment

Administration of a single 450 mg dose of RELISTOR tablets in subjects with mild, moderate, and severe hepatic impairment (6 subjects each of Child-Pugh Class A, B, and C) resulted in a 1.7-, 4.8- and 3.8-fold higher Cmaxof methylnaltrexone, respectively, compared to 6 subjects with normal liver function. The AUC0-∞, was comparable between healthy subjects and subjects with mild hepatic impairment, but increased approximately 2.1-fold in subjects with moderate and severe hepatic impairment [see Dosage and Administration (2.5)] .

Administration of a single dose of 0.3 mg/kg of RELISTOR injection subcutaneously in 8 subjects with mild hepatic impairment (Child-Pugh Class A) and 8 subjects with moderate hepatic impairment (Child-Pugh Class B) did not result in any meaningful change in the AUC or Cmaxwhen compared to 8 healthy subjects with normal hepatic function. The effect of severe (Child-Pugh Class C) hepatic impairment on the pharmacokinetics of RELISTOR injection has not been studied [see Dosage and Administration (2.5), Use in Specific Populations (8.7)] .

Drug Interaction Studies

Effect of Methylnaltrexone and its Metabolites on CYP Enzymes

In vitro,methylnaltrexone did not significantly inhibit or induce the activity of cytochrome P450 (CYP) isozymes CYP1A2, CYP2A6, CYP2B6, CYP2C9, CYP2C19, or CYP3A4. In addition, methylnaltrexone did not induce CYP2E1.

In vitro,the methylnaltrexone metabolites, methylnaltrexone sulfate, methyl-6α-naltrexol and methyl-6β-naltrexol did not inhibit CYP isozymes CYP1A2, CYP2B6, CYP2C8, CYP2C9, CYP2C19, CYP2D6, or CYP3A4. The metabolites of methylnaltrexone did not induce activity of CYP1A2, CYP2B6, or CYP3A4.

Effect of Methylnaltrexone and its Metabolites on Transporters

Based on the in vitrostudies, methylnaltrexone and its three major metabolites, methylnaltrexone sulfate, methyl-6α-naltrexol and methyl-6β-naltrexol, are unlikely to have clinically meaningful in vivodrug-drug interactions via inhibition of P-glycoprotein (P-gp), Breast Cancer Resistance Protein (BCRP), Multidrug Resistance Protein 2 (MRP2), Organic Anion-Transporting Polypeptide (OATP)1B1, OATP1B3, Organic Cation Transporter (OCT)1, OCT2, Organic Anion Transporter (OAT)1, OAT3, Multidrug and Toxic Extrusion Transporter (MATE)1 and MATE2-K at the recommended dosage of 450 mg orally or 12 mg subcutaneously once daily.

Methylnaltrexone: Methylnaltrexone was a substrate of OCT1, OCT2, MATE1, and MATE2-K, but not a substrate for P-gp, BCRP, MRP2, OATP1B1, OATP1B3, OAT1 and OAT3.

Methylnaltrexone sulfate: Methylnaltrexone sulfate was a substrate for MATE2-K and a potential substrate of BCRP, but was not a substrate of P-gp, MRP2, OATP1B1, OATP1B3, OCT1, OCT2, OAT1, OAT3, and MATE1.

Methyl-6α-naltrexol: Methyl-6α-naltrexol was a substrate of BCRP, OCT1, OCT2, MATE1, and MATE2-K, but was not a substrate of P-gp, MRP2, OATP1B1, OATP1B3, OAT1 and OAT3.

Methyl-6β-naltrexol: Methyl-6β-naltrexol was a substrate of OCT1, OCT2, MATE1, and MATE2-K, but was not a substrate of P-gp, BCRP, MRP2, OATP1B1, OATP1B3, OAT1 and OAT3.

Cimetidine

A clinical drug interaction study in healthy adult subjects evaluated the effects of cimetidine, a drug that inhibits the active renal secretion of organic cations, on the pharmacokinetics of methylnaltrexone (24 mg administered as an intravenous infusion over 20 minutes). A single dose of methylnaltrexone bromide was administered before cimetidine dosing and with the last dose of cimetidine (400 mg every 8 hours for 6 days). Mean Cmaxand AUC of methylnaltrexone increased by 10% with concomitant cimetidine administration. The renal clearance of methylnaltrexone decreased about 40%. This change is not considered to be clinically meaningful.

13 NONCLINICAL TOXICOLOGY

13.1 Carcinogenesis, Mutagenesis, Impairment of Fertility

Carcinogenesis

Two-year oral carcinogenicity studies have been conducted with methylnaltrexone bromide in CD-1 mice at doses up to 200 mg/kg/day (about 81 times the subcutaneous maximum recommended human dose (MRHD) of 12 mg/day based on body surface area) in males and 400 mg/kg/day (about 162 times the subcutaneous MRHD of 12 mg/day) in females and in Sprague Dawley rats at oral doses up to 300 mg/kg/day (about 243 times the subcutaneous MRHD of 12 mg/day). The 200 mg/kg/day and 400 mg/kg/day doses in male and female mice are about 2.2 and 4.4 times, respectively, the oral MRHD of 450 mg/day, and the 300 mg/kg/day dose in rats is about 6.5 times the oral MRHD of 450 mg/day, based on body surface area. Oral administration of methylnaltrexone bromide for 104 weeks did not produce tumors in mice and rats.

Mutagenesis

Methylnaltrexone bromide was negative in the Ames test, chromosome aberration tests in Chinese hamster ovary cells and human lymphocytes, in the mouse lymphoma cell forward mutation tests and in the in vivomouse micronucleus test.

Impairment of Fertility

Methylnaltrexone bromide at subcutaneous doses up to 150 mg/kg/day (about 122 times the subcutaneous MRHD of 12 mg/day; about 3.3 times the oral MRHD of 450 mg/day) was found to have no adverse effect on fertility and reproductive performance of male and female rats.

13.2 Animal Toxicology and/or Pharmacology

In an in vitro human cardiac potassium ion channel (hERG) assay, methylnaltrexone caused concentration-dependent inhibition of hERG current (1%, 12%, 13% and 40% inhibition at 30, 100, 300 and 1000 micromolar concentrations, respectively). Methylnaltrexone had a hERG IC50of more than 1000 micromolar. In isolated dog Purkinje fibers, methylnaltrexone caused prolongations in action potential duration (APD). The highest tested concentration (10 micromolar) in the dog Purkinje fiber study was about 18 and 37 times the Cmaxat human subcutaneous doses of 0.3 and 0.15 mg/kg, respectively. In isolated rabbit Purkinje fibers, methylnaltrexone (up to 100 micromolar) did not have an effect on APD, compared to vehicle control. The highest methylnaltrexone concentration (100 micromolar) tested was about 186 and 373 times the human Cmaxat subcutaneous doses of 0.3 and 0.15 mg/kg, respectively. In anesthetized dogs, methylnaltrexone bromide caused decreases in blood pressure, heart rate, cardiac output, left ventricular pressure, left ventricular end diastolic pressure, and +dP/dt at 1 mg/kg or more. In conscious dogs, methylnaltrexone bromide caused a dose-related increase in QTc interval. After a single intravenous dosage of 20 mg/kg to beagle dogs, predicted Cmaxand AUC values were approximately 482 and 144 times, respectively, the exposure at human subcutaneous dose of 0.15 mg/kg and 241 times and 66 times, respectively, the exposure at a human subcutaneous dose of 0.3 mg/kg. In conscious guinea pigs, methylnaltrexone bromide caused mild prolongation of QTc (4% over baseline) at 20 mg/kg, intravenous. A thorough QTc assessment was conducted in humans [see Clinical Pharmacology (12.2)] .

In juvenile rats administered intravenous methylnaltrexone bromide for 13 weeks, adverse clinical signs such as convulsions, tremors and labored breathing occurred at dosages of 3 and 10 mg/kg/day (about 2.4 and 8 times, respectively, the subcutaneous MRHD of 12 mg/day; about 0.06 and 0.22 times, respectively, the oral MRHD of 450 mg/day). Similar adverse clinical signs were seen in adult rats at 20 mg/kg/day (about 16 times the subcutaneous MRHD of 12 mg/day; about 0.43 times the oral MRHD of 450 mg/day). Juvenile rats were found to be more sensitive to the toxicity of methylnaltrexone bromide when compared to adults. The no observed adverse effect levels (NOAELs) in juvenile and adult rats were 1 and 5 mg/kg/day, respectively (about 0.8 and 4 times, respectively, the subcutaneous MRHD of 12 mg/day; about 0.02 and 0.11 times, respectively, the oral MRHD of 450 mg/day).

Juvenile dogs administered intravenous methylnaltrexone bromide for 13 weeks had a toxicity profile similar to adult dogs. Following intravenous administration of methylnaltrexone bromide for 13 weeks, decreased heart rate (13.2% reduction compared to pre-dose) in juvenile dogs and prolonged QTc interval in juvenile (9.6% compared to control) and adult (up to 15% compared to control) dogs occurred at 20 mg/kg/day (about 54 times the subcutaneous MRHD of 12 mg/day; about 1.5 times the oral MRHD of 450 mg/day). Clinical signs consistent with effects on the CNS (including tremors and decreased activity) occurred in both juvenile and adult dogs. The NOAELs in juvenile and adult dogs were 5 mg/kg/day (about 14 times the subcutaneous MRHD of 12 mg/day; about 0.4 times the oral MRHD of 450 mg/day).

14 CLINICAL STUDIES

14.1 Opioid-Induced Constipation in Adult Patients with Chronic Non-Cancer Pain

RELISTOR Tablets

The efficacy of RELISTOR tablets in the treatment of OIC in patients with chronic non-cancer pain was evaluated in a randomized, double-blind, placebo-controlled study (Study 1). This study compared 4-week treatment of RELISTOR tablets 450 mg orally once daily with placebo.

A total of 401 patients (200 RELISTOR, 201 placebo) were enrolled and treated in the double-blind period. Patients had a history of chronic non-cancer pain for which they were taking opioids. The most common pain condition requiring opioid use was back pain. Other frequently reported primary pain conditions were arthritis, neurologic/neuropathic pain, joint/extremity pain, and fibromyalgia. Prior to screening, patients were receiving opioid therapy for pain for 1 month or longer (median daily baseline oral morphine equivalent dose of 156 mg) and had OIC (less than 3 spontaneous bowel movements per week during the screening period). Constipation due to opioid use had to be associated with 1 or more of the following: A Bristol Stool Form Scale score of 1 or 2 for at least 25% of the bowel movements (BM), straining during at least 25% of the BMs or a sensation of incomplete evacuation after at least 25% of the BMs.

Patients were required to be on a stable opioid regimen (daily dose 50 mg or more of oral morphine equivalents per day) a minimum of 2 weeks prior to the screening visit and received their opioid medication during the study as clinically needed. The median duration of OIC at baseline was 53 months (4 years). The mean patient age was 52 years (range 23 to 78 years), 64% were female, and 84% of patients were Caucasian.

Eligible patients were required to discontinue all previous laxative therapy and use only the study-permitted rescue laxative (bisacodyl tablets). If patients did not have a bowel movement for 3 consecutive days during the study, they were permitted to use rescue medication (up to 3 bisacodyl tablets taken orally once during a 24-hour period). Bisacodyl tablets were taken 5 hours or longer and up to 8 hours after study drug administration. If rescue treatment with bisacodyl tablets did not result in a bowel movement, a second dose of bisacodyl or an enema 24 hours after rescue was permitted. Enema use was permitted after rescue with bisacodyl tablets had failed at least once.

A responder analysis was performed which defined the proportion of patients with 3 or more spontaneous bowel movements (SBMs)/week, with an increase of 1 or more SBM/week over baseline, for 3 or more out of the first 4 weeks of the treatment period. A SBM was defined as a bowel movement that occurred without laxative use during the previous 24 hours. Table 8presents the proportion of patients who responded during the double-blind treatment period in the intent-to-treat (ITT) population, which included all randomized patients who received at least one dose of double-blind study medication.

Table 8: Proportion of Responders* in the ITT Population in Study 1 of RELISTOR Tablets for the Treatment of OIC in Patients with Chronic Non-Cancer Pain
Treatment | N | n (%) | Percent Differencea; (2-sided 95% CI)
RELISTOR Tablets 450 mg Once Daily | 1. 200 | 103 (52%) | 13%; (3%, 23%)
Placebo | 1. 201 | 77 (38%) | 13%; (3%, 23%)

CI = confidence interval; ITT = intent-to-treat;
aDifference for active treatment vs. placebo;
*A responder is defined as a patient with 3 or more SBMs/week, with an increase of 1 or more SBM/week over baseline, for 3 or more out of the first 4 weeks of the treatment period.

RELISTOR Injection

The efficacy of RELISTOR injection in the treatment of OIC in patients with chronic non-cancer pain were evaluated in a randomized, double-blind, placebo-controlled study (Study 2). This study compared 4-week treatment of RELISTOR injection 12 mg administered subcutaneously once daily with placebo.

A total of 312 patients (150 RELISTOR, 162 placebo) were enrolled and treated in the double-blind period. Patients had a history of chronic non-cancer pain for which they were taking opioids. The majority of patients had a primary diagnosis of back pain; other primary diagnoses included joint/extremity pain, fibromyalgia, neurologic/neuropathic pain, and rheumatoid arthritis. Prior to screening, patients had been receiving opioid therapy for pain for 1 month or longer (median daily baseline oral morphine equivalent dose of 161 mg) and had OIC (less than 3 spontaneous bowel movements per week during the screening period). Constipation due to opioid use had to be associated with 1 or more of the following: A Bristol Stool Form Scale score of 1 or 2 for at least 25% of the bowel movements (BM), straining during at least 25% of the BMs or a sensation of incomplete evacuation after at least 25% of the BMs.

Patients were required to be on a stable opioid regimen (daily dose 50 mg or more of oral morphine equivalents per day) for at least 2 weeks before the screening visit and received their opioid medication during the study as clinically needed. The median duration of OIC at baseline was 59 months (5 years). The median patient age at baseline was 49 years, 62% were females and 90% were Caucasian.

Eligible patients were required to discontinue all previous laxative therapy and use only the study-permitted rescue laxative (bisacodyl tablets). If patients did not have a bowel movement for 3 consecutive days during the study, they were permitted to use rescue medication (up to 4 bisacodyl tablets taken orally once during a 24-hour period). Rescue laxatives were prohibited until at least 4 hours after taking an injection of study medication.

A responder analysis was performed which defined the proportion of patients with 3 or more (SBMs) per week for each of the 4 weeks of the double-blind period. A SBM was defined as a bowel movement that occurred without laxative use during the previous 24 hours. Table 9presents the proportion of patients who responded during the double-blind treatment period in the modified intent-to-treat (mITT) population, which included all randomized subjects who received at least one dose of double-blind study medication.

Table 9: Proportion of Responders* in the mITT Population in Study 2 of RELISTOR Injection for the Treatment of OIC in Patients with Chronic Non-Cancer Pain
Treatment | N | n (%) | Percent Differencea; (2-sided 95% CI) | P-valueb
RELISTOR Injection 12 mg Once Daily | - 150 | 88 (59%) | 20%; (10%, 31%) | <0.001
Placebo | - 162 | 62 (38%) | 20%; (10%, 31%) | <0.001

CI = confidence interval; mITT = modified intent-to-treat;

Following the first dose, 33% of patients in the RELISTOR treatment group had a SBM within 4 hours and approximately half of patients had a SBM prior to the second dose of RELISTOR injection.

14.2 Opioid-Induced Constipation in Adult Patients with Advanced Illness

The efficacy of RELISTOR injection in the treatment of OIC in advanced illness patients receiving palliative care was demonstrated in two randomized, double-blind, placebo-controlled studies. In these studies, the median age was 68 years (range 21 to 100 years); 51% were females. In both studies, patients had advanced illness and received care to control their symptoms. The majority of patients had a primary diagnosis of incurable cancer; other primary diagnoses included end-stage COPD/emphysema, cardiovascular disease/heart failure, Alzheimer's disease/dementia, HIV/AIDS, or other advanced illnesses. Prior to screening, patients had been receiving palliative opioid therapy (median daily baseline oral morphine equivalent dose of 172 mg), and had OIC (either less than 3 bowel movements in the preceding week or no bowel movement for 2 or more days). Patients were on a stable opioid regimen 3 or more days prior to randomization (not including PRN or rescue pain medication) and received their opioid medication during the study as clinically needed. Patients maintained their regular laxative regimen for at least 3 days prior to study entry, and throughout the study. Rescue laxatives were prohibited from 4 hours before to 4 hours after taking an injection of study medication.

Study 4 was a double-blind, placebo-controlled study which compared a single, subcutaneous dose of RELISTOR injection 0.15 mg/kg, and RELISTOR injection 0.3 mg/kg versus placebo. The double-blind dose was followed by an open-label 4-week dosing period, where RELISTOR injection could be used as needed, no more frequently than one dose in a 24-hour period. Throughout both study periods, patients maintained their regular laxative regimen. A total of 154 patients (47 RELISTOR 0.15 mg/kg, 55 RELISTOR 0.3 mg/kg, 52 placebo) were enrolled and treated in the double-blind period. The primary endpoint was the proportion of patients with a rescue-free laxation within 4 hours of the double-blind dose of study medication. RELISTOR-treated patients had a significantly higher rate of laxation within 4 hours of the double-blind dose (62% for 0.15 mg/kg and 58% for 0.3 mg/kg) than did placebo‑treated patients (14%); p <0.0001 for each dose versus placebo (Figure 1).

Study 5 was a double-blind, placebo-controlled study which compared subcutaneous doses of RELISTOR injection given every other day for 2 weeks versus placebo. Patients received opioid medication for at least 2 weeks prior to receiving study medication. During the first week (Days 1, 3, 5, 7) patients received either 0.15 mg/kg RELISTOR injection or placebo. In the second week the patient's assigned dose could be increased to 0.3 mg/kg if the patient had 2 or fewer rescue-free laxations up to Day 8. At any time, the patient's assigned dose could be reduced based on tolerability. Data from 133 (62 RELISTOR, 71 placebo) patients were analyzed. There were 2 primary endpoints: proportion of patients with a rescue-free laxation within 4 hours of the first dose of study medication and proportion of patients with a rescue-free laxation within 4 hours after at least 2 of the first 4 doses of study medication. RELISTOR-treated patients had a higher rate of laxation within 4 hours of the first dose (48%) than placebo-treated patients (16%); p <0.0001 (Figure 1). RELISTOR-treated patients also had significantly higher rates of laxation within 4 hours after at least 2 of the first 4 doses (52%) than did placebo-treated patients (9%); p <0.0001. In both studies, in approximately 30% of patients, laxation was reported within 30 minutes of a dose of RELISTOR.

Figure 1: Laxation Response within 4 Hours of the First Dose in Studies 4 and 5

In both studies, there was no evidence of differential effects of age or gender on safety or efficacy. No meaningful subgroup analysis could be conducted on race because the study population was predominantly Caucasian (88%).

Durability of Response

Durability of response was explored in Study 5, and the laxation response rate was consistent from dose 1 through dose 7 over the course of the 2-week, double-blind period.

The efficacy of RELISTOR injection was also demonstrated in open-label treatment administered from Day 2 through Week 4 in Study 4, and in two open-label extension studies (Study 4 EXT and Study 5 EXT) in which RELISTOR was given as needed for up to 4 months. During open-label treatment, patients maintained their regular laxative regimen. A total of 136, 21, and 82 patients received at least one open-label dose in Studies 4, 4 EXT, and 5 EXT, respectively. Laxation response was also explored in this open-label setting and appeared to be maintained over the course of 3 to 4 months of open-label treatment.

Opioid Use and Pain Scores

No relationship between baseline opioid dose and laxation response in RELISTOR-treated patients was identified in exploratory analyses of these studies. In addition, median daily opioid dose did not vary meaningfully from baseline in either RELISTOR-treated patients or in placebo-treated patients. There were no clinically relevant changes in pain scores from baseline in either the RELISTOR or placebo-treated patients.

16 HOW SUPPLIED/STORAGE AND HANDLING

How Supplied

NDC Number | Pack Size | Contents
65649-150-90 | 90-count bottle | 100-mL bottle containing 90 tablets and 2 silica gel desiccant canisters. Each 150 mg film-coated tablet is white, round, biconvex, and debossed with “REL” on one side and plain on the other side.
65649-551-02 | 1 vial per carton | One 12 mg/0.6 mL single-dose vial containing a colorless to pale yellow solution.
65649-552-04 | 7 pre-filled syringes per carton | Seven 8 mg/0.4 mL single-dose pre-filled syringes with needle guard system containing a colorless to pale yellow solution.
65649-551-03 | 7 pre-filled syringes per carton | Seven 12 mg/0.6 mL single-dose pre-filled syringes with needle guard system containing a colorless to pale yellow solution.
65649-551-07 | 1 pre-filled syringe per carton | One 12 mg/0.6 mL single-dose pre-filled syringe with needle guard system containing a colorless to pale yellow solution.

Storage

Tablets

Store at up to 25°C (77°F); excursions permitted to 15° to 30°C (59° to 86°F) [see USP Controlled Room Temperature].

Injection

Store at 20° to 25°C (68° to 77°F); excursions permitted to 15° to 30°C (59° to 86°F) [see USP Controlled Room Temperature].

Do not freeze. Protect from light.

17 PATIENT COUNSELING INFORMATION

Advise the patient to read the FDA-approved patient labeling (Medication Guide and Instructions for Use).

Administration

- Be within close proximity to toilet facilities once RELISTOR is administered.
- Discontinue RELISTOR if treatment with the opioid pain medication is also discontinued.
- Advise chronic non-cancer pain patients receiving RELISTOR for OIC to:
  - Discontinue all maintenance laxative therapy prior to initiation of RELISTOR. Laxative(s) can be used as needed if there is a suboptimal response to RELISTOR after 3 days.
  - Inform their healthcare provider if their opioid regimen is changed, to avoid adverse reactions, such as diarrhea.

Tablets

Advise patients with chronic non-cancer pain receiving RELISTOR tablets for OIC to take RELISTOR tablets once daily with water on an empty stomach at least 30 minutes before the first meal of the day.

Injection

- Advise all patients receiving RELISTOR injection to:
  - Inject RELISTOR subcutaneously in the upper arm, abdomen or thigh. Do not inject at the same spot each time (rotate injection sites).
  - Safely dispose of needles by following the sharps disposal recommendations described in the Instructions for Use.
- Advise chronic non-cancer pain patients receiving RELISTOR injection for OIC to inject one dose every day.
- Advise patients with advanced illness receiving RELISTOR injection for OIC to inject one dose every other day, as needed, but no more frequently than one dose in a 24-hour period.

Gastrointestinal Perforation

Advise patients to discontinue RELISTOR and to promptly seek medical attention if they develop unusually severe, persistent, or worsening abdominal pain [see Warnings and Precautions (5.1)] .

Severe or Persistent Diarrhea

Advise patients to discontinue RELISTOR if they experience severe or persistent diarrhea [ see Warnings and Precautions (5.2)].

Opioid Withdrawal

Advise patients that symptoms consistent with opioid withdrawal may occur while taking RELISTOR, including sweating, chills, diarrhea, abdominal pain, anxiety, and yawning [see Warnings and Precautions (5.3), Adverse Reactions (6.1)].

Pregnancy

Fetal Opioid Withdrawal

Advise females of reproductive potential, who become pregnant or are planning to become pregnant, that the use of RELISTOR during pregnancy may precipitate opioid withdrawal in a fetus due to the undeveloped blood-brain barrier [see Use in Specific Populations (8.1)] .

Lactation

Advise patients that breastfeeding is not recommended during treatment with RELISTOR [ see Use in Specific Populations (8.2)] .

Distributed by:
Salix
PHARMACEUTICALS

Salix Pharmaceuticals, a division of
Bausch Health US, LLC
Bridgewater, NJ 08807 USA

Under license from:
Progenics®
Pharmaceuticals

Progenics Pharmaceuticals, Inc.
Tarrytown, NY 10591 USA

For Injection: Patented. See https://patents.salix.com for US patent information.

For Tablets: Patented. See https://patents.salix.com for US patent information.

For more information, go to www.RELISTOR.com or call 1-800-321-4576.

RELISTOR is a trademark of Salix Pharmaceuticals, Inc. or its affiliates.

All other product/brand names and/or logos are trademarks of the respective owners.
© 2024 Salix Pharmaceuticals, Inc. or its affiliates
9502506
70014843-01

MEDICATION GUIDE

RELISTOR®(rel-i–store)
(methylnaltrexone bromide)
tablets
and
RELISTOR (rel-i–store)
(methylnaltrexone bromide)
injection, for subcutaneous use
What is the most important information I should know about RELISTOR?
RELISTOR can cause serious side effects, including:
- Tear in your stomach or intestinal wall (perforation).Stomach pain that is severe can be a sign of a serious medical condition. If you get stomach pain that is severe, does not go away, or gets worse, stop taking RELISTOR and get emergency medical help right away.
- Diarrhea that is severe or that will not go away.Stop taking RELISTOR and call your healthcare provider if you get diarrhea that is severe or that does not go away during treatment with RELISTOR.
- Opioid withdrawal.You may have symptoms of opioid withdrawal during treatment with RELISTOR including sweating, chills, diarrhea, stomach pain, anxiety, and yawning. Tell your healthcare provider if you have any of these symptoms.
What is RELISTOR?
RELISTOR is a prescription medicine used to treat constipation in adults that is caused by prescription pain medicines called opioids:
- RELISTOR tablets and RELISTOR injection are used to treat constipation caused by opioids in adults with long-lasting (chronic) pain that is not caused by active cancer.
- RELISTOR injection is used to treat constipation caused by opioids in adults with advanced illness or pain caused by active cancer and who need increases in their opioid dose for comfort care.
It is not known if RELISTOR is safe and effective in children.
Who should not use RELISTOR?
Do not use RELISTOR if youhave a bowel blockage (intestinal obstruction) or have a history of bowel blockage.
What should I tell my healthcare provider before taking RELISTOR?
Before you start taking RELISTOR, tell your healthcare provider about all of your medical conditions, including if you:
- have kidney problems.
- have liver problems.
- have any stomach or bowel (intestines) problems, including stomach ulcer, Crohn’s disease, diverticulitis, cancer of the stomach or bowel, or Ogilvie’s syndrome.
- are pregnant or plan to become pregnant. Taking RELISTOR during pregnancy may cause opioid withdrawal symptoms in your unborn baby. Tell your healthcare provider right away if you become pregnant during treatment with RELISTOR.
- are breastfeeding or plan to breastfeed. It is not known if RELISTOR passes into your breast milk. Taking RELISTOR while you are breastfeeding may cause opioid withdrawal in your baby. You should not breastfeed during treatment with RELISTOR.
Tell your healthcare provider about all of the medicines you take, including prescription and over-the-counter medicines, vitamins, and herbal supplements.
How should I take RELISTOR?
- Stay close to a toilet after taking RELISTOR.
- Stop taking RELISTOR if you stop taking your prescription opioid pain medicine. Tell your healthcare provider if your pain medicine changes.
- If you take too much RELISTOR, call your healthcare provider or go to the nearest emergency room right away.
- If you take RELISTOR for long-lasting (chronic) pain that is not caused by cancer:
- RELISTOR has been shown to be effective in people who have taken opioid pain medicines for at least 4 weeks to treat long-lasting (chronic) pain not caused by cancer.
- Stop taking other laxatives before you start treatment with RELISTOR. You may use other laxatives if RELISTOR does not work after 3 days of treatment.
Tablets:
- Take RELISTOR tablets 1 time each day with water. Take RELISTOR tablets on an empty stomach at least 30 minutes before your first meal of the day.
Injection (Vials and Pre-filled Syringes):
See the detailed “Instructions for Use” that comes with RELISTOR injection for information about how to prepare and inject RELISTOR injection, and properly throw away (dispose of) used needles and syringes the right way.
- RELISTOR injection is injected under the skin (subcutaneous injection) of the upper arm, stomach-area (abdomen), or thigh.
- Inject RELISTOR injection exactly as your healthcare provider tells you.
- If you use RELISTOR injection for long-lasting (chronic) pain that is not caused by cancer:
- Inject 1 dose of RELISTOR injection each day.
- If you use RELISTOR injection and are receiving treatment for advanced illness:
- Inject 1 dose of RELISTOR injection every other day, as needed. You should not inject more than 1 dose of RELISTOR injection in a 24-hour period.
What are the possible side effects of RELISTOR?
See “What is the most important information I should know about RELISTOR?”
- The most common side effects of RELISTOR tablets in people with long-lasting (chronic) pain that is not caused by cancer include:stomach-area (abdomen) pain, diarrhea, headache, swelling or a feeling of fullness or pressure in your abdomen, sweating, anxiety, muscle spasms, runny nose, and chills.
- The most common side effects of RELISTOR injection in people with long-lasting (chronic) pain that is not caused by cancer include:stomach-area (abdomen) pain, nausea, diarrhea, sweating, hot flush, tremor, and chills.
- The most common side effects of RELISTOR injection in people receiving treatment for their advanced illness include:stomach-area (abdomen) pain, gas, nausea, dizziness, and diarrhea.
Tell your healthcare provider if you have any side effect that bothers you or that does not go away. These are not all of the possible side effects of RELISTOR.
Call your doctor for medical advice about side effects. You may report side effects to FDA at 1-800-FDA-1088.
You may also report side effects to Salix Pharmaceuticals at 1-800-321-4576.
How should I store RELISTOR?
RELISTOR tablets:
- Store RELISTOR tablets at room temperature between 68° to 77°F (20° to 25°C).
- The bottle of RELISTOR tablets contains 2 desiccant canisters to help keep your medicine dry. Do not remove the desiccant canisters from the bottle.
RELISTOR injection (Vials and Pre-filled Syringes):
- Store RELISTOR vials and pre-filled syringes at room temperature between 68° to 77°F (20° to 25°C).
- Do not freeze RELISTOR vials or pre-filled syringes.
- Keep RELISTOR vials and pre-filled syringes away from light until you are ready to use them.
- If the contents of a RELISTOR vial have been drawn into a syringe and you are not able to use the medicine right away, keep the syringe at room temperature for up to 24 hours.
Keep RELISTOR and all medicines, needles and syringes out of the reach of children.
General information about the safe and effective use of RELISTOR
Medicines are sometimes prescribed for purposes other than those listed in a Medication Guide. Do not use RELISTOR for a condition for which it was not prescribed. Do not give RELISTOR to other people, even if they have the same symptoms that you have. It may harm them. You can ask your pharmacist or healthcare provider for information about RELISTOR that is written for health professionals.
What are the ingredients in RELISTOR tablets and RELISTOR injection?
Active ingredient:methylnaltrexone bromide
Inactive ingredients (tablets):silicified microcrystalline cellulose, microcrystalline cellulose, sodium lauryl sulfate, croscarmellose sodium, crospovidone, poloxamer 407, stearic acid (vegetable source), colloidal silicon dioxide, edetate calcium disodium, polyvinyl alcohol, titanium dioxide, polyethylene glycol and talc
Inactive ingredients (injection: vials and pre-filled syringes):sodium chloride USP, edetate calcium disodium USP, glycine hydrochloride. During manufacture, the pH may have been adjusted with hydrochloric acid and/or sodium hydroxide.
Distributed by:
Salix Pharmaceuticals, a division of
Bausch Health US, LLC
Bridgewater, NJ 08807 USA
Under license from:
Progenics Pharmaceuticals, Inc.
Tarrytown, NY 10591 USA
For Injection: Patented. See https://patents.salix.com for US patent information.
For Tablets: Patented. See https://patents.salix.com for US patent information.
For more information, go to www.RELISTOR.com or call 1-800-321-4576.
© 2024 Salix Pharmaceuticals, Inc. or its affiliates
This Medication Guide has been approved by the U.S. Food and Drug Administration.
Revised: May 2024
9502506 | 70014843-01

Instructions for Use – Pre-filled Syringe

INSTRUCTIONS FOR USE
RELISTOR®(rel-i-store)
(methylnaltrexone bromide)
injection, for subcutaneous use
Pre-filled Syringe

Read this Instructions for Use before you start using RELISTOR and each time you get a refill. There may be new information. This information does not take the place of talking to your healthcare provider about your medical condition or your treatment.

The following instructions explain how to prepare and give an injection of RELISTOR the right way, when using a pre-filled syringe of RELISTOR.

Important information:

- Do notuse a RELISTOR pre-filled syringe and attached needle more than 1 time, even if there is medicine left in the syringe. See Step 4 “Dispose of used pre-filled syringes and needles.”
- Safely throw away RELISTOR pre-filled syringes and attached needle after use.
- To avoid needle-stick injuries, do notrecap used needles.
- Avoid touching the trigger fingers of the RELISTOR pre-filled syringe to keep from activating the needle guard (safety device) too soon. The needle guard is activated by pressure from the plunger on the trigger fingers (See Figure A).

Gather the supplies you will need for your injection (See Figure A). These include:

- 1 RELISTOR pre-filled syringe with attached needle
- 1 alcohol swab
- 1 cotton ball or gauze
- 1 adhesive bandage
- a puncture resistant container, such as an FDA-cleared sharps disposal container to dispose of used pre-filled syringes and needles. See Step 4: “Dispose of used pre-filled syringes and needles.”

Step 1: Choose and prepare the injection site

- Choose an injection site on your stomach-area (abdomen), thighs, or upper arms. See the shaded areas in Figures B and C below. Do not inject at the exact same spot each time (rotate injection sites). Do not inject into areas where the skin is tender, bruised, red or hard. Avoid areas with scars or stretch marks.
- Figure B Abdomen or thigh– use these sites when injecting yourself or another person.
- Figure C Upper arm– use this site only when injecting another person.

- Clean the injection site with an alcohol swab and let it air dry. Do not touch this area again before giving the injection (See Figure D).

Step 2: Prepare the pre-filled syringe

- Choose a flat, clean, well-lit work surface.
- Wash your hands with soap and water before preparing for the injection.
- Look at the pre-filled syringe of RELISTOR (See Figure E). Make sure that the dose prescribed by your healthcare provider matches the dose on the pre-filled syringe label. Look at the plunger rod of the syringe. If the dose prescribed by your healthcare provider is 8 mg, the plunger rod will be yellow; if the prescribed dose is 12 mg, the plunger rod of the syringe will be dark blue (See Figure E).

- The liquid in the pre-filled syringe should be colorless to pale yellow, and should not have any particles in it. Do not use the pre-filled syringe if it looks discolored, cloudy, or has any particles.
- Use one hand to firmly hold the barrel of the pre-filled syringe. Use your other hand to pull the needle cap straight off (See Figure F). Do not touch the needle or allow it to touch anything.

Step 3: Inject RELISTOR

- Use one hand to pinch the skin around the injection site (See Figure G).

- Use your other hand to hold the pre-filled syringe. Insert the full length of the needle into the skin at a 45-degree angle with a quick “dart-like” motion (See Figure H).

- Let go of the skin and slowly push the plunger in with your thumb until the pre-filled syringe is empty (See Figure I). This will release the needle guard (safety device).

- Continue to hold pressure on the plunger with your thumb and quickly pull the needle out of the skin. Be careful to keep the needle at the same angle as it was inserted. Remove your thumb from the plunger to allow the protective sleeve to cover the needle (See Figure J). There may be a little bleeding at the injection site.

- Hold a cotton ball or gauze over the injection site (See Figure K). Do not rub the injection site. Apply an adhesive bandage to the injection site if needed.

Step 4: Dispose of used pre-filled syringes and needles

- Do notuse the pre-filled syringe and attached needle.
- To avoid needle-stick injuries, do notrecap used needles.
- Put your used pre-filled syringes and attached needles in an FDA-cleared sharps disposal container right away after use. Do not throw away (dispose of) loose needles and syringes in your household trash.
- If you do not have an FDA-cleared sharps disposal container, you may use a household container that is:
- made of a heavy-duty plastic,
- can be closed with a tight-fitting, puncture-resistant lid, without sharps being able to come out,
- upright and stable during use,
- leak-resistant, and
- properly labeled to warn of hazardous waste inside the container.
- When your sharps disposal container is almost full, you will need to follow your community guidelines for the right way to dispose of your sharps disposal container. There may be state or local laws about how you should throw away used needles and syringes. For more information about safe sharps disposal, and for specific information about sharps disposal in the state that you live in, go to the FDA’s website at: http://www.fda.gov/safesharpsdisposal.
- Do not dispose of your used sharps disposal container in your household trash unless your community guidelines permit this. Do not recycle your used sharps disposal container.
- If you have any questions, talk to your healthcare provider or pharmacist.

How should I store RELISTOR?

- Store pre-filled syringes at room temperature between 68° to 77°F (20° to 25°C).
- Do not freeze RELISTOR.
- Keep RELISTOR away from light until you are ready to use it.

Keep RELISTOR and all medicines, needles and syringes out of the reach of children.

For more information, go to www.Relistor.com or call 1-800-321-4576.

Distributed by:
Salix
Pharmaceuticals

Salix Pharmaceuticals, a division of
Bausch Health US, LLC
Bridgewater, NJ 08807 USA

Under license from:
Progenics®
Pharmaceuticals

Progenics Pharmaceuticals, Inc.
Tarrytown, NY 10591 USA
For Injection: Patented. See https://patents.salix.com for US patent information.
For Tablets: Patented. See https://patents.salix.com for US patent information.
RELISTOR is a trademark of Salix Pharmaceuticals, Inc. or its affiliates.
All other product/brand names and/or logos are trademarks of the respective owners.
© 2024 Salix Pharmaceuticals, Inc. or its affiliates
This Instructions for Use has been approved by the U.S. Food and Drug Administration.
Revised: 05/2024
9502506
70014843-01

Instructions for Use - Vial and Syringe with Retractable Needle in Tray

INSTRUCTIONS FOR USE
RELISTOR®(rel-i-store)
(methylnaltrexone bromide)
injection, for subcutaneous use
Vial and Syringe with Retractable Needle in Tray

Read this Instructions for Use before you start using RELISTOR and each time you get a refill. There may be new information. This information does not take the place of talking to your healthcare provider about your medical condition or your treatment.

The following instructions explain how to prepare and give an injection of RELISTOR the right way, when using a RELISTOR tray containing a syringe with a retractable needle. A retractable needle is one that is pulled back so that it is covered after use, to prevent needle-stick injury.

Important information:

- Do notuse a RELISTOR vial more than 1 time, even if there is medicine left in the vial.
- If RELISTOR has been drawn into a syringe and you are unable to use the medicine right away, carefully recap the needle and keep the syringe at room temperature for up to 24 hours. For more information about how to store RELISTOR, see the section called “How should I store RELISTOR?”at the end of this Instructions for Use.
- Safely throw away RELISTOR vials after use.
- Do notreuse syringes and needles. See Step 5: “Dispose of used syringes and needles”for information about how to safely throw away used needles and syringes.
- To avoid needle-stick injuries, do not recap used needles.

Your tray should include (See Figure A):

- 1 RELISTOR vial
- 1 1 mL syringe with retractable needle (VanishPoint)
- 2 alcohol swabs
- You will also need:
- 1 cotton ball or gauze
- 1 adhesive bandage
- a puncture resistant container, such as an FDA-cleared sharps disposal container to dispose of your used syringes and needles. See Step 5: “Dispose of used syringes and needles.”

Step 1: Choose and prepare the injection site

- Choose an injection site on your stomach-area (abdomen), thighs, or upper arms. See the shaded areas in Figures and C below. Do not inject at the exact same spot each time (rotate injection sites). Do not inject into areas where the skin is tender, bruised, red, or hard. Avoid areas with scars or stretch marks.
- Figure B Abdomen or thigh– use these sites when injecting yourself or another person.
- Figure C Upper arm– use this site only when injecting another person.

- Clean the injection site with an alcohol swab and let it air dry. Do not touch this area again before giving the injection (See Figure D).

Step 2: Prepare the injection

- Choose a flat, clean, well-lit work surface.
- Wash your hands with soap and water before preparing for the injection.
- Look at the vial of RELISTOR (See Figure E). The liquid in the vial should be colorless to pale yellow, and should not have any particles in it. Do not use the vial if it looks discolored, cloudy, or has any particles.

Step 3: Prepare the syringe

- Remove the cap from the vial containing RELISTOR (See Figure F).

- Wipe the rubber stopper with an alcohol swab (See Figure G).

- Firmly hold the barrel of the syringe with one hand. With your other hand, pull the needle cap straight off (See Figure H). Do not touch the needle or allow it to touch anything.

- Carefully pull back on the plunger to the line that matches the dose prescribed by your healthcare provider (See Figures I and J). For most people, this will be the 0.4 mL mark which is an 8 mg dose or the 0.6 mL mark which is a 12 mg dose.
- Use one hand to hold the vial steady. Use your other hand to insert the needle straight down into the rubber top of the RELISTOR vial (See Figure K). Do not insert it at an angle. This may cause the needle to bend or break. You will feel some resistance as the needle passes through the rubber top.

- Gently push down on the plunger until you feel resistance, and most of the air has gone from the syringe into the vial (See Figure L). Stop pushing down on the plunger when you feel resistance. If you continue to push down on the plunger when you feel resistance, the needle will pull back (retract) into the syringe barrel.

- With the needle still in the vial, turn the vial and syringe upside down. Hold the syringe at eye level. Make sure the tip of the needle is in the fluid. Slowly pull back on the plunger (See Figure M) until the top of the plunger lines up with the mark that matches your prescribed dose. For most people, this will be the 0.4 mL mark which is an 8 mg dose or the 0.6 mL mark which is a 12 mg dose.

- You may see some fluid or bubbles inside the vial when the syringe is filled. This is normal.
- With the needle still in the vial, gently tap the syringe to make any air bubbles rise to the top (See Figure N).

- Gently push the plunger up until all air bubbles are out of the syringe (See Figure O). A small air bubble may stay in the syringe. This is okay and it will not affect the dose of medicine in the syringe.

- Make sure the tip of the needle is in the fluid. Slowly pull back the plunger to draw the right amount of liquid back into the syringe (See Figure P).

Check to be sure that you have the right dose of RELISTOR in the syringe.

- Slowly withdraw the needle from the vial. Do not touch the needle or allow it to touch anything. Safely throw away the vial with any unused medicine.

Step 4: Inject RELISTOR

- Use one hand to pinch the skin around the injection site (See Figure Q).

- Use your other hand to hold the syringe. Insert the full length of the needle into the skin at a 45-degree angle with a quick “dart-like” motion (See Figure R).

- Let go of the skin and slowly push in on the plunger past the resistance point, until the syringe is empty and you hear a click (See Figure S).

- The click sound means that the needle (See Figure T) has been pulled back (retracted) into the syringe barrel (See Figure U). You can now remove the syringe from your skin.

- Hold a cotton ball or gauze over the injection site (See Figure V). Do not rub the injection site. Apply an adhesive bandage to the injection site if needed.

Step 5: Dispose of used syringes and needles

- Do notre-use syringes or needles.
- To avoid needle-stick injuries, do notrecap used needles.
- Put your used needles and syringes in an FDA-cleared sharps disposal container right away after use. Do not throw away (dispose of) loose needles and syringes in your household trash.
- If you do not have an FDA-cleared sharps disposal container, you may use a household container that is:
- made of a heavy-duty plastic,
- can be closed with a tight-fitting, puncture-resistant lid, without sharps being able to come out,
- upright and stable during use,
- leak-resistant, and
- properly labeled to warn of hazardous waste inside the container.
- When your sharps disposal container is almost full, you will need to follow your community guidelines for the right way to dispose of your sharps disposal container. There may be state or local laws about how you should throw away used needles and syringes. For more information about safe sharps disposal, and for specific information about sharps disposal in the state that you live in, go to the FDA’s website at: http://www.fda.gov/safesharpsdisposal.
- Do not dispose of your used sharps disposal container in your household trash unless your community guidelines permit this. Do not recycle your used sharps disposal container.
- If you have any questions, talk to your healthcare provider or pharmacist.

How should I store RELISTOR?

- Store RELISTOR vials at room temperature between 68° to 77°F (20° to 25°C).
- Do not freeze RELISTOR.
- Keep RELISTOR away from light until you are ready to use it.
- If RELISTOR has been drawn into a syringe and you are unable to use the medicine right away, keep the syringe at room temperature for up to 24 hours.

Keep RELISTOR and all medicines, needles and syringes out of the reach of children.

For more information, go to www.Relistor.com or call 1-800-321-4576.

Distributed by:
Salix
Pharmaceuticals

Salix Pharmaceuticals, a division of
Bausch Health US, LLC
Bridgewater, NJ 08807 USA

Under license from:
Progenics®
Pharmaceuticals

Progenics Pharmaceuticals, Inc.
Tarrytown, NY 10591 USA

For Injection: Patented. See https://patents.salix.com for US patent information.
For Tablets: Patented. See https://patents.salix.com for US patent information.
RELISTOR is a trademark of Salix Pharmaceuticals, Inc. or its affiliates.
All other product/brand names and/or logos are trademarks of the respective owners.
© 2024 Salix Pharmaceuticals, Inc. or its affiliates
This Instructions for Use has been approved by the U.S. Food and Drug Administration.
Revised: 05/2024
9502506
70014843-01

Instructions for Use - Vial

INSTRUCTIONS FOR USE
RELISTOR® (rel-i-store)
(methylnaltrexone bromide)
injection, for subcutaneous use
Vial

Read this Instructions for Use before you start using RELISTOR and each time you get a refill. There may be new information. This information does not take the place of talking to your healthcare provider about your medical condition or your treatment.

The following instructions explain how to prepare and give an injection of RELISTOR the right way, when using a vial of RELISTOR.

Important information:

- Use the syringes and needles prescribed by your healthcare provider.
- Do notuse a RELISTOR vial more than 1 time, even if there is medicine left in the vial.
- If RELISTOR has been drawn into a syringe and you are unable to use the medicine right away, carefully recap the needle and keep the syringe at room temperature for up to 24 hours. For more information about how to store RELISTOR, see the section “How should I store RELISTOR?”at the end of this Instructions for Use.
- Safely throw away RELISTOR vials after use.
- Do notre-use syringes or needles. See Step 5 “Dispose of used syringes and needles”for information about how to safely throw away used needles and syringes.
- To avoid needle-stick injuries, do notrecap used needles.

Gather the supplies you will need for your injection (See Figure A.). These include:

- 1 RELISTOR vial
- 1 1 mL syringe with a 27-gauge, ½ inch needle for subcutaneous use
- 2 alcohol swabs
- 1 cotton ball or gauze
- 1 adhesive bandage
- a puncture resistant container, such as an FDA-cleared sharps disposal container to dispose of used syringes and needles. See Step 5: “Dispose of used syringes and needles.”

Step 1: Choose and prepare the injection site

- Choose an injection site on your stomach-area (abdomen), thighs, or upper arms. See the shaded areas in Figures B and C below. Do not inject at the exact same spot each time (rotate injection sites). Do not inject into areas where the skin is tender, bruised, red or hard. Avoid areas with scars or stretch marks.
- Figure B Abdomen or thigh– use these sites when injecting yourself or another person.
- Figure C Upper arm– use this site only when injecting another person.

- Clean the injection site with an alcohol swab and let it air dry. Do not touch this area again before giving the injection (See Figure D).

Step 2: Prepare the injection

- Choose a flat, clean, well-lit work surface.
- Wash your hands with soap and water before preparing for the injection.
- Look at the vial of RELISTOR (See Figure E). The liquid in the vial should be colorless to pale yellow, and should not have any particles in it. Do not use the vial if it looks discolored, cloudy, or has any particles.

Step 3: Prepare the syringe

- Remove the cap from the RELISTOR vial (See Figure F).

- Wipe the rubber stopper with an alcohol swab (See Figure G).

- Firmly hold the barrel of the syringe with one hand. With your other hand, pull the needle cap straight off (See Figure H). Do not touch the needle or allow it to touch anything.

- Carefully pull back on the plunger to the line that matches the dose prescribed by your healthcare provider (See Figures I and J). For most people, this will be the 0.4 mL mark which is an 8 mg dose or the 0.6 mL mark which is a 12 mg dose.
- Use one hand to hold the vial steady. Use your other hand to insert the needle straight down into the rubber top of the vial (See Figure K). Do not insert it at an angle. This may cause the needle to bend or break. You will feel some resistance as the needle passes through the rubber top.

- Gently push down the plunger until all of the air has gone from the syringe into the vial (See Figure L).

- With the needle still in the vial, turn the vial and syringe upside down. Hold the syringe at eye level. Make sure the tip of the needle is in the fluid. Slowly pull back on the plunger (See Figure M) until the top of the plunger lines up with the mark that matches your prescribed dose. For most people, this will be the 0.4 mL mark which is an 8 mg dose or the 0.6 mL mark which is a 12 mg dose.

- You may see some fluid or bubbles inside the vial when the syringe is filled. This is normal.
- With the needle still in the vial, gently tap the side of the syringe to make any air bubbles rise to the top (See Figure N).

- Slowly push the plunger up until all air bubbles are out of the syringe (See Figure O). A small air bubble may stay in the syringe. This is okay and it will not affect the dose of medicine in the syringe.

- Make sure the tip of the needle is in the fluid. Slowly pull back the plunger to draw the right amount of liquid back into the syringe (See Figure P).

Check to be sure that you have the right dose of RELISTOR in the syringe.

- Slowly withdraw the needle from the vial. Do not touch the needle or allow it to touch anything. Safely throw away the vial with any unused medicine.

Step 4: Inject RELISTOR

- Use one hand to pinch the skin around the injection site (See Figure Q).

- Use your other hand to hold the syringe. Insert the full length of the needle into the skin at a 45-degree angle with a quick “dart-like” motion (See Figure R).

- Let go of the skin and slowly push in on the plunger until the syringe is empty (Figure S).

- When the syringe is empty, quickly pull the needle out of the skin, being careful to keep it at the same angle as it was inserted. There may be a little bleeding at the injection site.
- Hold a cotton ball or gauze over the injection site (Figure T). Do not rub the injection site. Apply an adhesive bandage to the injection site if needed.

Step 5: Dispose of used syringes and needles

- Do notre-use a syringe or needle.
- To avoid needle-stick injuries, do notrecap a used needle.
- Put your used needles and syringes in an FDA-cleared sharps disposal container right away after use. Do not throw away (dispose of) loose needles and syringes in your household trash.
- If you do not have an FDA-cleared sharps disposal container, you may use a household container that is:
- made of a heavy-duty plastic,
- can be closed with a tight-fitting, puncture-resistant lid, without sharps being able to come out,
- upright and stable during use,
- leak-resistant, and
- properly labeled to warn of hazardous waste inside the container.
- When your sharps disposal container is almost full, you will need to follow your community guidelines for the right way to dispose of your sharps disposal container. There may be state or local laws about how you should throw away used needles and syringes. For more information about safe sharps disposal, and for specific information about sharps disposal in the state that you live in, go to the FDA’s website at: http://www.fda.gov/safesharpsdisposal.
- Do not dispose of your used sharps disposal container in your household trash unless your community guidelines permit this. Do not recycle your used sharps disposal container.
- If you have any questions, talk to your healthcare provider or pharmacist.

How should I store RELISTOR?

- Store RELISTOR vials at room temperature between 68° to 77°F (20° to 25°C).
- Do not freeze RELISTOR.
- Keep RELISTOR away from light until you are ready to use it.
- If RELISTOR has been drawn into a syringe and you are unable to use the medicine right away, keep the syringe at room temperature for up to 24 hours.

Keep RELISTOR and all medicines, needles and syringes out of the reach of children.

For more information, go to www.Relistor.com or call 1-800-321-4576.

Distributed by:

Salix Pharmaceuticals, a division of

Bausch Health US, LLC

Bridgewater, NJ 08807 USA

Under license from:

Progenics Pharmaceuticals, Inc.

Tarrytown, NY 10591 USA

1. For Injection: Patented. See https://patents.salix.com for US patent information.
  For Tablets: Patented. See https://patents.salix.com for US patent information.
  RELISTOR is a trademark of Salix Pharmaceuticals, Inc. or its affiliates.
  All other product/brand names and/or logos are trademarks of the respective owners.
  © 2024 Salix Pharmaceuticals, Inc. or its affiliates
  This Instructions for Use has been approved by the U.S. Food and Drug Administration.
  Revised: 05/2024
  9502506
  70014843-01

PRINCIPAL DISPLAY PANEL - 12 mg/0.6 mL

NDC65649-551-03

Rx only

RELISTOR ®
(methylnaltrexone bromide)
Subcutaneous Injection

12 mg/0.6 ml per syringe
PHARMACIST: Dispense the enclosed
Medication Guide to each patient.

For Subcutaneous Injection Only

Contains 7 Pre-filled Syringes with Needle Guard
Single Use Only. Discard after use.

Protect syringe from light.

Salix
Pharmaceuticals

PRINCIPAL DISPLAY PANEL - 8 mg/0.4 mL

NDC65649-552-04

Rx only

RELISTOR®
(methylnaltrexone bromide)
Subcutaneous Injection

8 mg/0.4 mL per syringe

PHARMACIST: Dispense the enclosed
Medication Guide to each patient.

For Subcutaneous Injection Only

Contains 7 Pre-filled Syringes with Needle Guard
Single Use Only. Discard after use.

Protect syringe from light.

PRINCIPAL DISPLAY PANEL – 150 mg Tablets

NDC65649-150-90

RELISTOR®

(methylnaltrexone bromide) Tablets

150 mg

Dispense the accompanying Medication Guide to each patient.

Rx only

90 Tablets